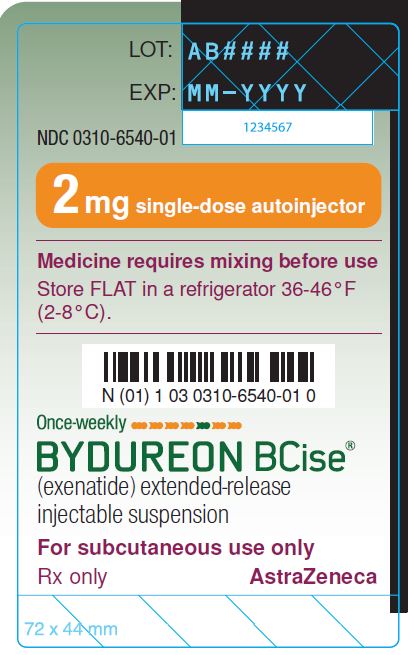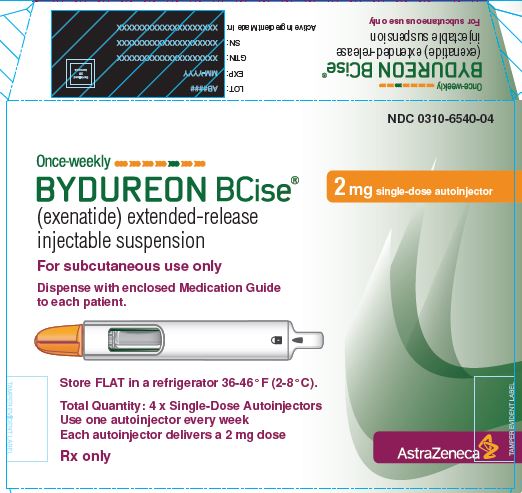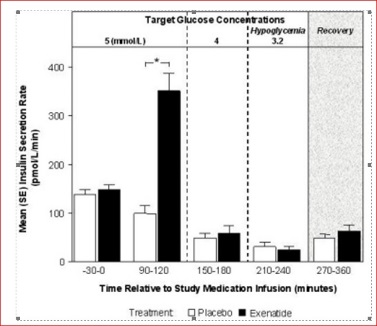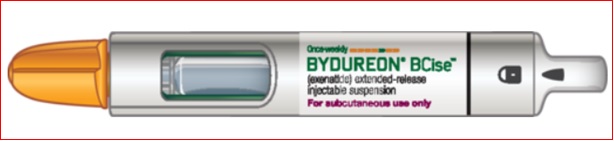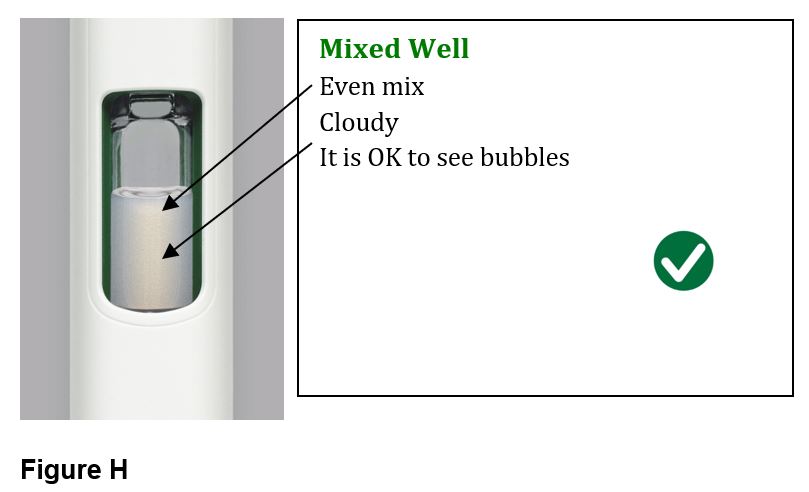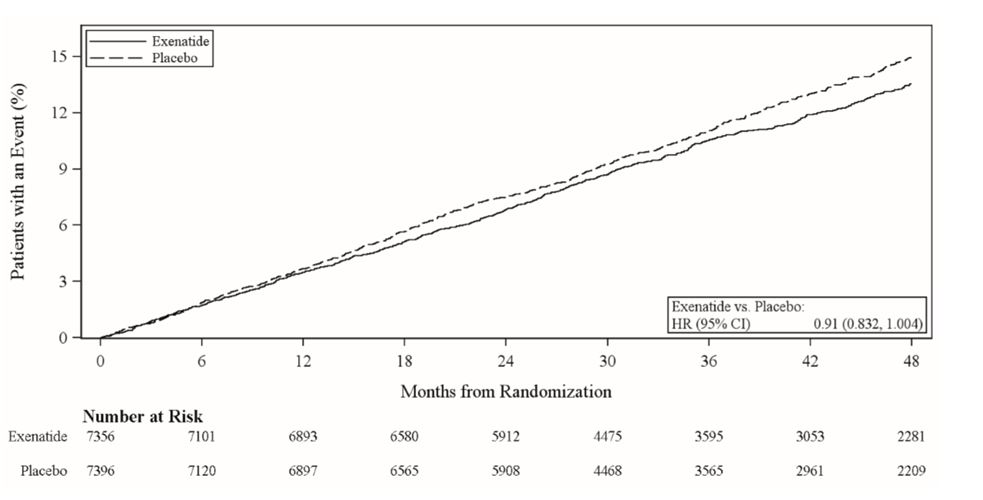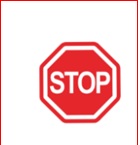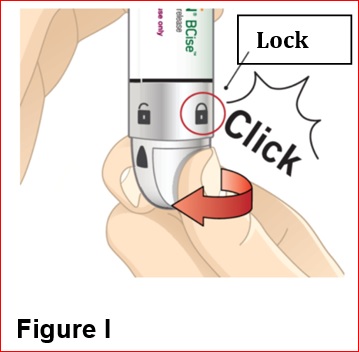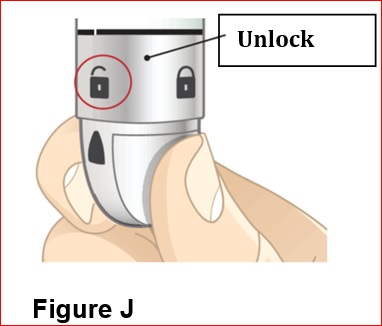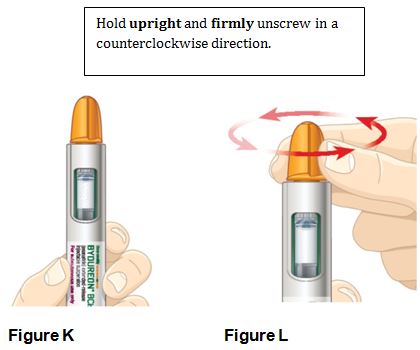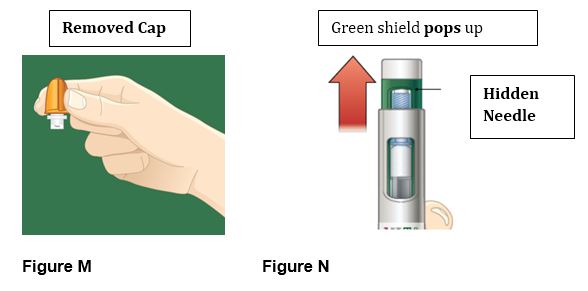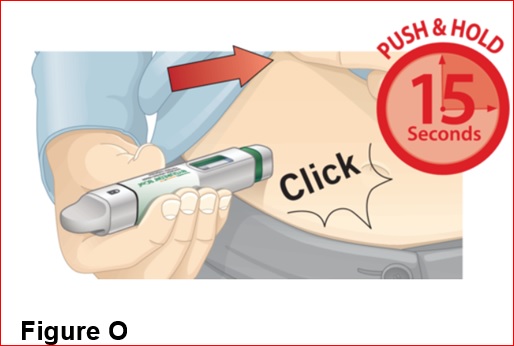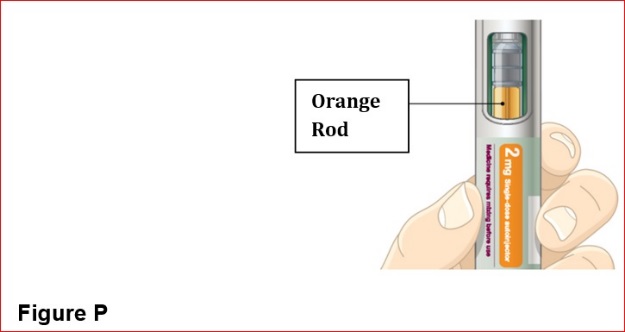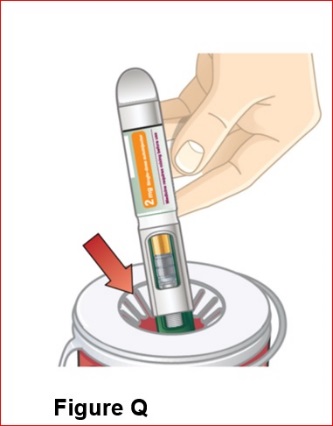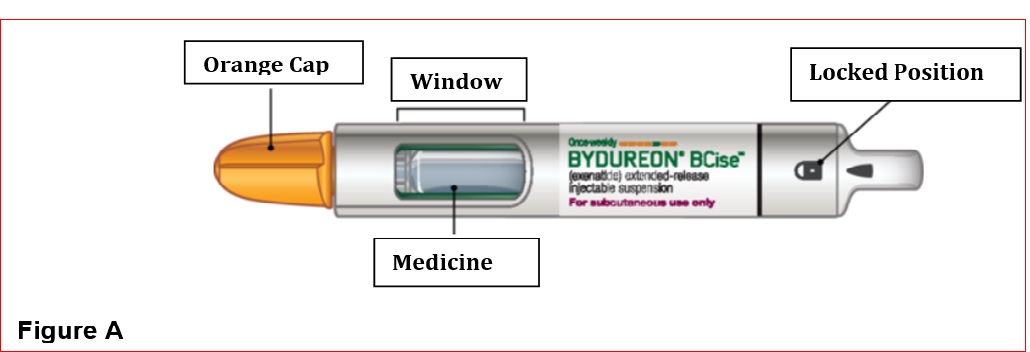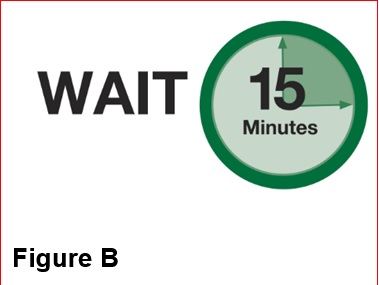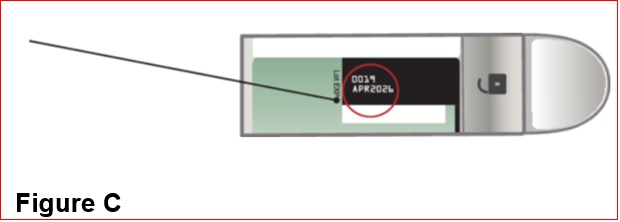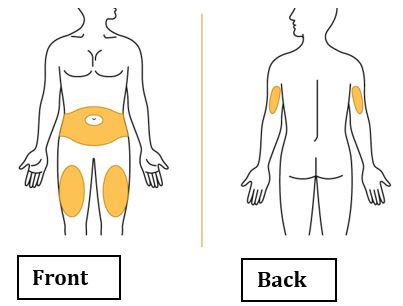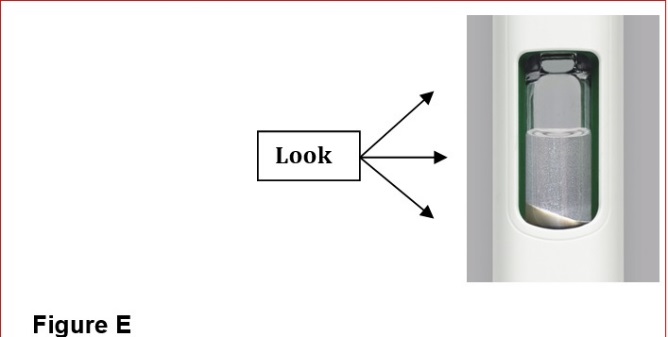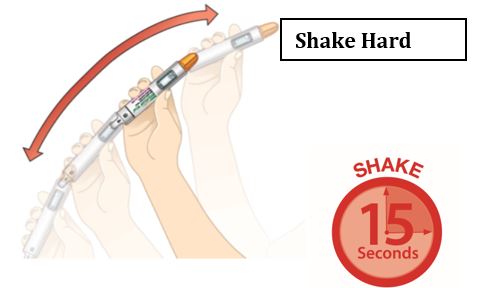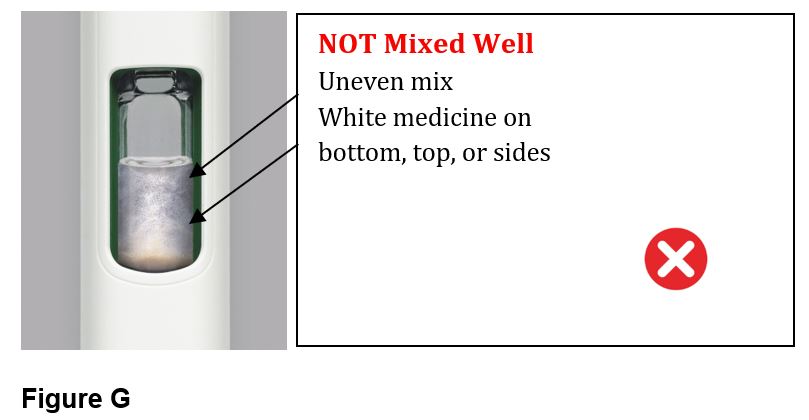 DRUG LABEL: BYDUREON BCise
NDC: 0310-6540 | Form: INJECTION, SUSPENSION, EXTENDED RELEASE
Manufacturer: AstraZeneca Pharmaceuticals LP
Category: prescription | Type: HUMAN PRESCRIPTION DRUG LABEL
Date: 20250528

ACTIVE INGREDIENTS: EXENATIDE 2 mg/0.85 mL
INACTIVE INGREDIENTS: DL-LACTIDE AND GLYCOLIDE (50:50) COPOLYMER 63000 ACID; SUCROSE; MEDIUM-CHAIN TRIGLYCERIDES

HIGHLIGHTS OF PRESCRIBING INFORMATION

These highlights do not include all the information needed to use BYDUREON BCISE safely and effectively. See full prescribing information for BYDUREON BCISE.
BYDUREON BCISE® (exenatide) extended-release injectable suspension, for subcutaneous use
Initial U.S. Approval: 2005

RECENT MAJOR CHANGES

Warnings and Precautions, Pulmonary Aspiration During General Anesthesia or Deep Sedation (5.11) 11/2024

WARNING: RISK OF THYROID C-CELL TUMORS

See full prescribing information for complete boxed warning.

- Exenatide extended-release causes thyroid C-cell tumors at clinically relevant exposures in rats. It is unknown whether BYDUREON BCISE causes thyroid C-cell tumors, including medullary thyroid carcinoma (MTC) in humans, as the human relevance of exenatide extended-release-induced rodent thyroid C-cell tumors has not been determined. (5.1, 13.1)
- BYDUREON BCISE is contraindicated in patients with a personal or family history of MTC or in patients with Multiple Endocrine Neoplasia syndrome type 2 (MEN 2). Counsel patients regarding the potential risk of MTC and the symptoms of thyroid tumors. (4, 5.1)

1 INDICATIONS AND USAGE

BYDUREON BCISE is a glucagon-like peptide-1 (GLP-1) receptor agonist indicated as an adjunct to diet and exercise to improve glycemic control in adults and pediatric patients aged 10 years and older with type 2 diabetes mellitus. (1)

Limitations of Use:

- Coadministration with other exenatide containing products is not recommended. (1)

2 DOSAGE AND ADMINISTRATION

- Administer 2 mg by subcutaneous injection once every seven days (weekly), at any time of day and with or without meals. (2.1)
- Administer immediately after the dose is prepared. See full prescribing information for additional administration instructions. (2.2)

3 DOSAGE FORMS AND STRENGTHS

Extended-release injectable suspension: 2 mg of exenatide in a 0.85 mL single-dose autoinjector. (3)

4 CONTRAINDICATIONS

- Personal or family history of medullary thyroid carcinoma or in patients with Multiple Endocrine Neoplasia syndrome type 2. (4)
- Prior serious hypersensitivity reaction to exenatide or any of the product components. (4)
- History of drug-induced immune-mediated thrombocytopenia from exenatide products. (4)

5 WARNINGS AND PRECAUTIONS

- Acute Pancreatitis: Has been observed in patients treated with GLP-1 receptor agonists, including BYDUREON BCISE. Discontinue if pancreatitis is suspected. (5.2)
- Hypoglycemia with Concomitant Use of Insulin Secretagogues or Insulin: Patients taking an insulin secretagogue or insulin may have an increased risk of hypoglycemia, including severe hypoglycemia. Reduction in the dose of insulin secretagogues or insulin may be necessary. (5.3)
- Acute Kidney Injury Due to Volume Depletion: Monitor renal function in patients reporting adverse reactions that could lead to volume depletion. (5.4)
- Severe Gastrointestinal Adverse Reactions: Use has been associated with gastrointestinal adverse reactions, sometimes severe. BYDUREON BCISE is not recommended in patients with severe gastroparesis. (5.5)
- Immunogenicity-Associated Decreased Glycemic Control: Patients may develop antibodies to exenatide. If there is worsening glycemic control or failure to achieve target glycemic control, consider alternative antidiabetic therapy. (5.6)
- Hypersensitivity Reactions: Serious hypersensitivity reactions (e.g., anaphylaxis and angioedema) have been reported. Discontinue BYDUREON BCISE and promptly seek medical advice. (5.7)
- Drug-induced Immune-mediated Thrombocytopenia: Serious bleeding which may be fatal has been reported. Discontinue BYDUREON BCISE promptly and avoid re-exposure to exenatide. (5.8)
- Serious Injection-site Reactions: Serious injection-site reactions with or without subcutaneous nodules have been reported. (5.9)
- Acute Gallbladder Disease: If cholelithiasis or cholecystitis are suspected, gallbladder studies are indicated. (5.10)
- Pulmonary Aspiration During General Anesthesia or Deep Sedation: Has been reported in patients receiving GLP-1 receptor agonists undergoing elective surgeries or procedures. Instruct patients to inform healthcare providers of any planned surgeries or procedures. (5.11)

6 ADVERSE REACTIONS

Most common (≥5%) in clinical trials: injection-site nodule, nausea. (6.1)

To report SUSPECTED ADVERSE REACTIONS, contact AstraZeneca at 1-800-236-9933 and www.bydureonbcise.com or FDA at 1-800-FDA-1088 or www.fda.gov/medwatch.

7 DRUG INTERACTIONS

- May impact absorption of orally administered medications. (7)
- Warfarin: Postmarketing reports with exenatide of increased international normalized ratio (INR) sometimes associated with bleeding. Monitor INR frequently until stable upon initiation of BYDUREON BCISE therapy. (7)

8 USE IN SPECIFIC POPULATIONS

- Pregnancy: Use during pregnancy only if the potential benefit justifies the risk to the fetus. (8.1)

FULL PRESCRIBING INFORMATION

WARNING: RISK OF THYROID C-CELL TUMORS

- Exenatide extended-release causes an increased incidence in thyroid C-cell tumors at clinically relevant exposures in rats compared to controls. It is unknown whether BYDUREON BCISE causes thyroid C-cell tumors, including medullary thyroid carcinoma (MTC), in humans, as the human relevance of exenatide extended-release-induced rodent thyroid C-cell tumors has not been determined [see Warnings and Precautions (5.1) and Nonclinical Toxicology (13.1)].
- BYDUREON BCISE is contraindicated in patients with a personal or family history of MTC and in patients with Multiple Endocrine Neoplasia syndrome type 2 (MEN 2). Counsel patients regarding the potential risk for MTC with the use of BYDUREON BCISE and inform them of symptoms of thyroid tumors (e.g., mass in the neck, dysphagia, dyspnea, persistent hoarseness). Routine monitoring of serum calcitonin or using thyroid ultrasound is of uncertain value for detection of MTC in patients treated with BYDUREON BCISE [see Contraindications (4) and Warnings and Precautions (5.1)].

1 INDICATIONS AND USAGE

BYDUREON BCISE is indicated as an adjunct to diet and exercise to improve glycemic control in adults and pediatric patients aged 10 years and older with type 2 diabetes mellitus.

Limitations of Use

- BYDUREON BCISE contains exenatide. Coadministration with other exenatide-containing products is not recommended.

2 DOSAGE AND ADMINISTRATION

2.1 Recommended Dosage

- The recommended dosage of BYDUREON BCISE is 2 mg subcutaneously once every 7 days (weekly). The dose can be administered at any time of day, with or without meals.
- Discontinue an immediate- or extended-release exenatide product prior to initiation of BYDUREON BCISE. Patients changing from another extended-release exenatide product to BYDUREON BCISE may do so at the next regularly scheduled dose. Patients changing from immediate-release exenatide to BYDUREON BCISE may experience transient (approximately 2 to 4 weeks) elevations in blood glucose concentrations.
- The day of weekly administration can be changed if necessary, as long as the last dose was administered 3 or more days before the new day of administration.

Recommendations Regarding Missed Dose

- If a dose is missed, administer the dose as soon as noticed, provided the next regularly scheduled dose is due at least 3 days later. Thereafter, administer subsequent doses once every 7 days (weekly).
- If a dose is missed and the next regularly scheduled dose is due 1 or 2 days later, do not administer the missed dose and instead resume BYDUREON BCISE with the next regularly scheduled dose.

2.2 Administration Instructions

- Prior to initiation, train patients and caregivers on proper mixing and injection [see Instructions for Use]. Instruct caregivers to assist pediatric patients with mixing and administration.
- Remove the autoinjector from the refrigerator 15 minutes prior to mixing the injection, in order to reach room temperature.
- Mix by shaking vigorously for at least 15 seconds.
- Inspect BYDUREON BCISE visually before use. After mixing, BYDUREON BCISE should appear as an opaque, cloudy, white to off-white suspension, evenly mixed with no residual medicine along the side, bottom or top of the inspection window. Do not use if particulate matter is present or if discoloration is observed.
- Administer BYDUREON BCISE immediately after the autoinjector is prepared as a subcutaneous injection in the abdomen, thigh, or upper arm region. Advise patients to use a different injection site each week when injecting in the same region.
- When using BYDUREON BCISE with insulin, instruct patients to administer as separate injections and to never mix the products. It is acceptable to inject BYDUREON BCISE and insulin in the same body region, but the injections should not be adjacent to each other.

3 DOSAGE FORMS AND STRENGTHS

Extended-release injectable suspension: 2 mg of exenatide per 0.85 mL suspension, in a pre-filled single-dose autoinjector. Redispersion by mixing provides a white to off-white, opaque, suspension.

4 CONTRAINDICATIONS

BYDUREON BCISE is contraindicated in patients with a:

- Personal or family history of medullary thyroid carcinoma (MTC) or in patients with Multiple Endocrine Neoplasia syndrome type 2 (MEN 2).
- Prior serious hypersensitivity reaction to exenatide or to any of the excipients of BYDUREON BCISE. Serious hypersensitivity reactions including anaphylactic reactions and angioedema have been reported with exenatide [see Warnings and Precautions (5.7)].
- History of drug-induced immune-mediated thrombocytopenia from exenatide products. Serious bleeding, which may be fatal, from drug-induced immune-mediated thrombocytopenia has been reported with exenatide use [see Warnings and Precautions (5.8)].

5 WARNINGS AND PRECAUTIONS

5.1 Risk of Thyroid C-cell Tumors

In both genders of rats, exenatide extended-release caused a dose-related and treatment-duration–dependent increase in the incidence of thyroid C-cell tumors (adenomas and/or carcinomas) at clinically relevant exposures compared to controls [see Nonclinical Toxicology (13.1)]. A statistically significant increase in malignant thyroid C-cell carcinomas was observed in female rats receiving exenatide extended-release at 27-times clinical exposure compared to controls and higher incidences were noted in males above controls in all treated groups at ≥2-times clinical exposure. The potential of exenatide extended-release to induce C-cell tumors in mice has not been evaluated. Other glucagon-like peptide-1 (GLP-1) receptor agonists have also induced thyroid C-cell adenomas and carcinomas in male and female mice and rats at clinically relevant exposures. It is unknown whether BYDUREON BCISE will cause thyroid C-cell tumors, including medullary thyroid carcinoma (MTC), in humans as the human relevance of exenatide extended-release-induced rodent thyroid C-cell tumors has not been determined.

Cases of MTC in patients treated with liraglutide, another GLP-1 receptor agonist, have been reported in the postmarketing period; the data in these reports are insufficient to establish or exclude a causal relationship between MTC and GLP-1 receptor agonist use in humans.

BYDUREON BCISE is contraindicated in patients with a personal or family history of MTC or in patients with MEN 2. Counsel patients regarding the potential risk of MTC with the use of BYDUREON BCISE and inform them of symptoms of thyroid tumors (e.g., a mass in the neck, dysphagia, dyspnea, persistent hoarseness).

Routine monitoring of serum calcitonin or using thyroid ultrasound is of uncertain value for early detection of MTC in patients treated with BYDUREON BCISE. Such monitoring may increase the risk of unnecessary procedures, due to the low specificity of serum calcitonin testing for MTC and a high background incidence of thyroid disease. Significantly elevated serum calcitonin may indicate MTC and patients with MTC usually have values >50 ng/L. If serum calcitonin is measured and found to be elevated, the patient should be further evaluated. Patients with thyroid nodules noted on physical examination or neck imaging should also be further evaluated.

5.2 Acute Pancreatitis

Acute pancreatitis, including fatal and non-fatal hemorrhagic or necrotizing pancreatitis, has been observed in patients treated with GLP-1 receptor agonists, including BYDUREON BCISE [see Adverse Reactions (6)]. After initiation of BYDUREON BCISE, observe patients carefully for signs and symptoms of pancreatitis (including persistent severe abdominal pain, sometimes radiating to the back and which may or may not be accompanied by vomiting). If pancreatitis is suspected, discontinue BYDUREON BCISE and initiate appropriate management.

5.3 Hypoglycemia with Concomitant Use of Insulin Secretagogues or Insulin

Patients receiving BYDUREON BCISE in combination with an insulin secretagogue (e.g., sulfonylurea) or insulin may have an increased risk of hypoglycemia, including severe hypoglycemia [see Adverse Reactions (6.1) and Drug Interactions (7)].

The risk of hypoglycemia may be lowered by a reduction in the dose of sulfonylurea (or other concomitantly administered insulin secretagogues) or insulin. Inform patients using these concomitant medications of the risk of hypoglycemia and educate them on the signs and symptoms of hypoglycemia.

5.4 Acute Kidney Injury Due to Volume Depletion

There have been postmarketing reports of acute kidney injury, in some cases requiring hemodialysis, in patients treated with GLP-1 receptor agonists, including BYDUREON BCISE [see Adverse Reactions (6.2)]. The majority of the reported events occurred in patients who experienced gastrointestinal reactions leading to dehydration such as nausea, vomiting, or diarrhea [see Adverse Reactions (6)]. Monitor renal function in patients reporting adverse reactions to BYDUREON BCISE that could lead to volume depletion, especially when initiating BYDUREON BCISE.

BYDUREON BCISE is not recommended for use in patients with an eGFR below 45 mL/min/1.73 m2 [see Use in Specific Populations (8.6)].

5.5 Severe Gastrointestinal Adverse Reactions DOCVARIABLE vault_nd_fcd34bb4-3cb3-473c-864a-ed4ae529f642 \* MERGEFORMAT

Use of GLP-1 receptor agonists, including BYDUREON BCISE, has been associated with gastrointestinal adverse reactions, sometimes severe [see Adverse Reactions (6)]. BYDUREON BCISE is not recommended in patients with severe gastroparesis.

5.6 Immunogenicity-Associated Decreased Glycemic Control

In the 28-week treatment period in Trials 1 and 2 in adult patients with type 2 diabetes mellitus [see Clinical Studies (14.2)], BYDUREON BCISE-treated patients who had high titer anti-exenatide antibodies (defined as ≥625) had a lower glycemic response compared to BYDUREON BCISE-treated patients who did not have anti-exenatide antibodies [see Clinical Pharmacology (12.6)].

In the 24-week treatment period in Trial 9 in pediatric patients with type 2 diabetes mellitus [see Clinical Studies (14.6)], BYDUREON-treated patients who had high titer anti-exenatide antibodies (≥625) appeared to have had a lower glycemic response compared to BYDUREON-treated patients who did not have anti-exenatide antibodies. At Week 24, the mean change in HbA1c from baseline in BYDUREON-treated patients was greater (-0.73%) in those with low titer anti-exenatide antibodies (<625) compared to +0.07% in those with high titer anti-exenatide antibodies [see Clinical Pharmacology (12.6)].

If there is worsening glycemic control or failure to achieve targeted glycemic control, consider stopping BYDUREON BCISE and using alternative antidiabetic therapy.

5.7 Hypersensitivity Reactions

There have been postmarketing reports of serious hypersensitivity reactions (e.g., anaphylaxis and angioedema) in patients treated with exenatide. If a hypersensitivity reaction occurs, the patient should discontinue BYDUREON BCISE and promptly seek medical advice [see Contraindications (4) and Adverse Reactions (6.2)]. Inform and closely monitor patients with a history of anaphylaxis or angioedema with another GLP‑1 receptor agonist for allergic reactions, because it is unknown whether such patients will be predisposed to anaphylaxis with BYDUREON BCISE.

5.8 Drug-Induced Thrombocytopenia

Serious bleeding, which may be fatal, from drug-induced immune-mediated thrombocytopenia has been reported in the postmarketing setting with exenatide use. Drug-induced thrombocytopenia is an immune-mediated reaction with exenatide-dependent anti-platelet antibodies. In the presence of exenatide, these antibodies cause platelet destruction. If drug-induced thrombocytopenia is suspected, discontinue BYDUREON BCISE immediately and do not re-expose the patient to exenatide. Upon discontinuation, thrombocytopenia can persist due to the prolonged exenatide exposure from BYDUREON BCISE (about 10 weeks) [see Adverse Reactions (6.2)].

5.9 Serious Injection-Site Reactions

There have been postmarketing reports of serious injection-site reactions (e.g., abscess, cellulitis, and necrosis), with or without subcutaneous nodules, with the use of BYDUREON [see Adverse Reactions (6.2)]. Isolated cases required surgical intervention.

5.10 Acute Gallbladder Disease

Acute events of gallbladder disease, such as cholelithiasis or cholecystitis, have been reported in GLP-1 receptor agonist trials and postmarketing. In the EXSCEL trial [see Clinical Studies (14.5)], 1.9% of BYDUREON-treated patients and 1.4% of placebo-treated patients reported an acute event of gallbladder disease, such as cholelithiasis or cholecystitis. If cholelithiasis is suspected, gallbladder studies and appropriate clinical follow-up are indicated.

5.11 Pulmonary Aspiration During General Anesthesia or Deep Sedation

BYDUREON BCISE delays gastric emptying [see Clinical Pharmacology (12.2)]. There have been rare postmarketing reports of pulmonary aspiration in patients receiving GLP-1 receptor agonists undergoing elective surgeries or procedures requiring general anesthesia or deep sedation who had residual gastric contents despite reported adherence to preoperative fasting recommendations.

Available data are insufficient to inform recommendations to mitigate the risk of pulmonary aspiration during general anesthesia or deep sedation in patients taking BYDUREON BCISE, including whether modifying preoperative fasting recommendations or temporarily discontinuing BYDUREON BCISE could reduce the incidence of retained gastric contents. Instruct patients to inform healthcare providers prior to any planned surgeries or procedures if they are taking BYDUREON BCISE.

6 ADVERSE REACTIONS

The following serious adverse reactions are described below or elsewhere in the prescribing information:

- Risk of Thyroid C-cell Tumors [see Warnings and Precautions (5.1)]
- Acute Pancreatitis [see Warnings and Precautions (5.2)]
- Hypoglycemia with Concomitant Use of Insulin Secretagogues or Insulin [see Warnings and Precautions (5.3)]
- Acute Kidney Injury Due to Volume Depletion [see Warnings and Precautions (5.4)]
- Severe Gastrointestinal Adverse Reactions [see Warnings and Precautions (5.5)]
- Immunogenicity-Associated Decreased Glycemic Control [see Warnings and Precautions (5.6)]
- Hypersensitivity Reactions [see Warnings and Precautions (5.7)]
- Drug-Induced Thrombocytopenia [see Warnings and Precautions (5.8)]
- Serious Injection-Site Reactions [see Warnings and Precautions (5.9)]
- Acute Gallbladder Disease [see Warnings and Precautions (5.10)]
- Pulmonary Aspiration During General Anesthesia or Deep Sedation [see Warnings and Precautions (5.11)]

6.1 Clinical Trial Experience

Because clinical trials are conducted under widely varying conditions, adverse reaction rates observed in the clinical trials of a drug cannot be directly compared to rates in the clinical trials of another drug and may not reflect the rates observed in practice.

The data in this section are derived from pooled data from the controlled period of the 2 comparator-controlled trials (Trials 1 and 2) in adults as well as data from the extension phase of one of these trials [see Clinical Studies (14.2)]. There were 410 patients exposed to BYDUREON BCISE 2 mg for 28 weeks during the controlled phases, and an additional 116 patients exposed to BYDUREON BCISE 2 mg during an uncontrolled extension for an additional 24 weeks. Overall, there were 526 patients exposed to BYDUREON BCISE 2 mg with a mean duration of exposure of 35 weeks in the controlled and extension phases of the two trials. Across the treatment arms in the controlled periods, the mean age of patients was 55 years, 2% were 75 years or older and 59% were male. The population in these studies was 78% White, 15% Black or African American, 5% Asian; 1% American Indian or Alaska Native; <1 % were Native Hawaiian or Pacific Islander; and <1% were other races. This population included 42% of Hispanic or Latino ethnicity. At baseline, the population had diabetes for an average of 8.3 years and had a mean HbA1c of 8.5%. Baseline estimated renal function was normal or mildly impaired (eGFR ≥60 mL/min/1.73 m^2) in 93% of the pooled study populations.

The safety of BYDUREON, another formulation of exenatide extended-release, in pediatric patients age 10 to less than 18 years with type 2 diabetes was similar to that observed in the adults [see Clinical Studies (14.6)].

Common Adverse Reactions

Table 1 summarizes the adverse reactions with an incidence ≥5% occurring in BYDUREON BCISE-treated adult patients in the pooled data from the controlled and extension phases, including 10 weeks of follow‑up, of the two comparator-controlled 28-week clinical trials. Adverse reactions were identified based on known adverse reactions associated with BYDUREON.

Table 1: Adverse Reactions Reported in ≥5% of BYDUREON BCISE-Treated Patients from Pooled Clinical Trial Data in Patients with Type 2 Diabetes Mellitus (Trials 1 and 2)
 | BYDUREON BCISE; 2 mg; N=526; %
Injection site nodule | 10.5
Nausea | 8.2
Note: Percentages are based on the number of patients who were randomized and received at least one dose of BYDUREON BCISE.

Nausea was a common adverse reaction associated with initiation of treatment with BYDUREON BCISE and usually decreased over time with continued use. The incidence of nausea and/or vomiting was 2% in the first week of therapy compared to 1% in the 4th week of therapy.

Less Common Adverse Reactions

Adverse reactions that occurred in >2% and <5% of adult patients receiving BYDUREON BCISE during the controlled and extension phases, including 10 weeks of follow‑up, of the two comparator-controlled 28-week clinical trials include: headache (4.4%), diarrhea (4.0%), vomiting (3.4%), injection site pruritus (3.2%), dizziness (2.5%), injection site erythema (2.3%), constipation (2.1%).

Adverse Reactions Leading to Discontinuation of Therapy

The incidence of discontinuation of therapy due to adverse reactions was 3.9% for BYDUREON BCISE-treated patients in the two comparator-controlled 28-week trials in adults. The most common classes of adverse reactions leading to discontinuation of therapy for BYDUREON BCISE-treated patients were Gastrointestinal Disorders 2.0% and General Disorders and Administration Site Conditions 1.2%. For BYDUREON BCISE-treated patients, the most frequent adverse reactions leading to discontinuation of therapy within each of these respective classes were diarrhea (0.7%), nausea (0.7%), vomiting (0.5%) and injection-site nodule (0.5%).

Hypoglycemia

Table 2 summarizes the incidence of glucose level <54 mg/dL regardless of hypoglycemia clinical symptoms and the incidence of severe hypoglycemia in the two comparator-controlled 28-week trials of BYDUREON BCISE in adults.

Table 2: Incidence (% of Subjects) of Hypoglycemia (glucose <54 mg/dL) and Severe Hypoglycemia in Clinical Trials in Patients with Type 2 Diabetes Mellitus
Incidence of Hypoglycemia (glucose <54 mg/dL)
Mono- or Combination Therapy with One or Two OADs Trial (28 weeks)
With Concomitant Sulfonylurea Use
BYDUREON BCISE 2 mg (N=88) | 25%
Without Concomitant Sulfonylurea Use
BYDUREON BCISE 2 mg (N=141) | 2.1%
Add-On to Metformin Trial (28 weeks)
All treated subjects
BYDUREON BCISE 2 mg (N=181) | 0.0%
Incidence of Severe Hypoglycemia
Mono- or Combination Therapy with One or Two OADs Trial (28 weeks)
With Concomitant Sulfonylurea Use
BYDUREON BCISE 2 mg (N=88) | 2.3%
Without Concomitant Sulfonylurea Use
BYDUREON BCISE 2 mg (N=141) | 0.7%
Add-On to Metformin Trial (28 weeks)
All treated subjects
BYDUREON BCISE 2 mg (N=181) | 0.0%
Note: N and percentages are based on the number of patients who were randomized and received at least one dose of BYDUREON BCISE.

Severe hypoglycemia was defined as clinical symptoms that were considered to result from hypoglycemia in which the patient required the assistance of another person and associated with recovery after oral carbohydrates, intravenous glucose or glucagon administration if no plasma glucose was available.

In the 24-week pediatric placebo-controlled clinical trial [see Clinical Studies (14.6)], 2 (3.4%) of BYDUREON-treated patients with type 2 diabetes had hypoglycemia with a blood glucose <54 mg/dL with or without symptoms and 1 (1.7%) had severe hypoglycemia (defined as an episode with severe cognitive impairment requiring external assistance for recovery.

Injection-Site Adverse Reactions Including Nodules

In the two comparator-controlled 28-week trials in adults, injection site reactions (including injection site nodule, injection site pruritus, injection site bruising) were observed in 23.9% of patients treated with BYDUREON BCISE.

Immunogenicity: Anti-Drug Antibody-Associated Adverse Reactions

Injection site reactions for BYDUREON BCISE-treated patients were more commonly observed in those with high titer anti-exenatide antibodies (≥625) (27%) compared to those with low titer anti-exenatide antibodies (<625) (16%) or those who did not develop anti-exenatide antibodies (16%) [see Clinical Pharmacology (12.6)].

Increase in Heart Rate

In clinical trials of BYDUREON BCISE in adults, the mean increase from baseline in heart rate was 2.4 beats per minute.

Acute Pancreatitis

In clinical trials of BYDUREON BCISE acute pancreatitis occurred in 0.4% of patients.

Cholelithiasis and cholecystitis

In the EXSCEL trial [see Clinical Studies (14.5)], 1.9% of BYDUREON-treated patients and 1.4% of placebo-treated patients reported an acute event of gallbladder disease, such as cholelithiasis or cholecystitis.

6.2 Postmarketing Experience

The following adverse reactions have been identified during post-approval use of BYDUREON BCISE or other formulations of exenatide. Because these reactions are reported voluntarily from a population of uncertain size, it is not always possible to reliably estimate their frequency or establish a causal

Blood: Drug induced thrombocytopenia.

Drug Interactions: Increased international normalized ratio (INR) sometimes associated with bleeding, with concomitant warfarin [see Drug Interactions (7)].

Gastrointestinal: Nausea, vomiting, and/or diarrhea resulting in dehydration; abdominal distension, abdominal pain, eructation, constipation, flatulence, ileus, acute pancreatitis, hemorrhagic and necrotizing pancreatitis sometimes resulting in death.

Hepatobiliary: Cholecystitis, cholelithiasis requiring cholecystectomy.

Hypersensitivity: Injection-site reactions (e.g., abscess, cellulitis, and necrosis, with or without subcutaneous nodules), generalized pruritus and/or urticaria, macular or papular rash, angioedema; anaphylactic reaction.

Neurologic: Dysgeusia, somnolence, dysesthesia.

Pulmonary: Pulmonary aspiration has occurred in patients receiving GLP-1 receptor agonists undergoing elective surgeries or procedures requiring general anesthesia or deep sedation.

Renal: Altered renal function, including increased serum creatinine, renal impairment, worsened chronic renal failure or acute renal failure (sometimes requiring hemodialysis), kidney transplant and kidney transplant dysfunction.

Skin and Subcutaneous Tissue: Alopecia.

7 DRUG INTERACTIONS

Table 3: Clinically Relevant Interactions with BYDUREON BCISE
Concomitant Use of Insulin Secretagogues or Insulin
Clinical Impact | Exenatide promotes insulin release from pancreatic beta-cells in the presence of elevated glucose concentrations. The risk of hypoglycemia is increased when exenatide is used in combination with insulin secretagogues (e.g., sulfonylureas) or insulin [see Adverse Reactions (6.1)].
Intervention | When initiating BYDUREON BCISE, consider reducing the dose of concomitantly administered insulin secretagogue or insulin to reduce the risk of hypoglycemia.
Warfarin
Clinical Impact | BYDUREON BCISE has not been studied with warfarin. However, in a drug interaction study, BYETTA did not have a significant effect on INR [see Clinical Pharmacology (12.3)]. There have been postmarketing reports for exenatide of increased INR with concomitant use of warfarin, sometimes associated with bleeding [see Adverse Reactions (6.2)].
Intervention | In patients taking warfarin, the INR should be monitored more frequently after initiating BYDUREON BCISE. Once a stable INR has been documented, the INR can be monitored at the intervals recommended for patients taking warfarin.
Orally Administered Drugs (e.g., acetaminophen)
Clinical Impact | Exenatide slows gastric emptying. Therefore, BYDUREON BCISE has the potential to reduce the rate of absorption of orally administered drugs [see Clinical Pharmacology (12.3)].
Intervention | Use caution when administering oral medications with BYDUREON BCISE where a slower rate of oral absorption may be clinically meaningful.

8 USE IN SPECIFIC POPULATIONS

8.1 Pregnancy

Risk Summary

Limited data with exenatide, the active ingredient in BYDUREON BCISE, in pregnant women are not sufficient to determine a drug-associated risk for major birth defects or miscarriage. There are risks to the mother and fetus associated with poorly controlled diabetes in pregnancy (see Clinical Considerations). Based on animal reproduction studies, there may be risks to the fetus from exposure to BYDUREON BCISE during pregnancy. BYDUREON BCISE should be used during pregnancy only if the potential benefit justifies the potential risk to the fetus.

Animal reproduction studies identified increased adverse fetal and neonatal outcomes from exposure to exenatide extended-release during pregnancy or from exposure to exenatide during pregnancy and lactation, in association with maternal effects. In rats, exenatide extended-release, administered during the period of organogenesis, reduced fetal growth and produced skeletal ossification deficits at doses that approximate clinical exposures at the maximum recommended human dose (MRHD) of 2 mg/week. In mice, exenatide administered during gestation and lactation, caused increased neonatal deaths at doses that approximate clinical exposures at the MRHD (see Data). Based on animal data, advise pregnant women of the potential risk to a fetus.

The estimated background risk of major birth defects is 6-10% in women with pre-gestational diabetes with an HbA1c >7 and has been reported to be as high as 20-25% in women with HbA1c >10. The estimated background risk of miscarriage for the indicated population is unknown. In the U.S. general population, the estimated background risk of major birth defects and miscarriage in clinically recognized pregnancies is 2-4% and 15-20%, respectively.

Clinical Considerations

Disease-associated Maternal and/or Embryofetal Risk

Poorly controlled diabetes in pregnancy increases the maternal risk for diabetic ketoacidosis, preeclampsia, spontaneous abortions, preterm delivery and delivery complications. Poorly controlled diabetes increases the fetal risk for major birth defects, stillbirth, and macrosomia-related morbidity.

Data

Animal Data

Pregnant rats given subcutaneous doses of 0.3, 1, or 3 mg/kg exenatide extended-release every 3 days during organogenesis had systemic exposures 3-, 8-, and 19-times human exposure, respectively, at the MRHD of 2 mg/week BYDUREON BCISE based on plasma exenatide exposure (AUC) comparison. Reduced fetal growth at all doses and skeletal ossification deficits at 1 and 3 mg/kg occurred at doses that decreased maternal food intake and body weight gain.

In studies evaluating reproduction and development in pregnant mice and rabbits, maternal animals were administered exenatide, the active ingredient in BYDUREON BCISE, by subcutaneous injection twice a day. Differences in embryofetal developmental toxicity from subcutaneously injected exenatide extended-release and exenatide were not evaluated in mice, rats, or rabbits.

In pregnant mice given 6, 68, 460, or 760 mcg/kg/day exenatide during fetal organogenesis, skeletal variations associated with slowed fetal growth, including changes in number of rib pairs or vertebral ossifications sites, and wavy ribs were observed at 760 mcg/kg/day, a dose that produced maternal toxicity and yielded systemic exposure 200-times the human exposure resulting from the MRHD of BYDUREON BCISE based on AUC comparison.

In pregnant rabbits given 0.2, 2, 22, 156, or 260 mcg/kg/day exenatide during fetal organogenesis, irregular fetal skeletal ossifications were observed at 2 mcg/kg/day, a dose yielding systemic exposure up to 6-times the human exposure from the MRHD of BYDUREON BCISE based on AUC comparison.

In maternal mice given 6, 68, or 760 mcg/kg/day exenatide from gestation day 6 through lactation day 20 (weaning), an increased number of neonatal deaths at 6 mcg/kg/day were observed on postpartum days 2 to 4 in dams given 6 mcg/kg/day, a dose yielding a systemic exposure equivalent to the human exposure from the MRHD of BYDUREON BCISE based on AUC comparison.

8.2 Lactation

Risk Summary

There is no information regarding the presence of exenatide, in human milk, the effects of exenatide on the breastfed infant, or the effects of exenatide on milk production. Exenatide, the active ingredient in BYDUREON BCISE was present in the milk of lactating mice. However, due to species-specific differences in lactation physiology, the clinical relevance of these data is not clear (see Data). The developmental and health benefits of breastfeeding should be considered along with the mother’s clinical need for exenatide and any potential adverse effects on the breastfed child from exenatide or from the underlying maternal condition.

Data

In lactating mice subcutaneously injected twice a day with exenatide, the active ingredient in BYDUREON BCISE, the concentration of exenatide in milk was up to 2.5% of the concentration in maternal plasma.

8.4 Pediatric Use

The safety and effectiveness of BYDUREON BCISE as an adjunct to diet and exercise to improve glycemic control in type 2 diabetes mellitus have been established in pediatric patients aged 10 years and older. Use of BYDUREON BCISE for this indication is supported by a 24-week placebo-controlled trial with BYDUREON with 28-week open-label uncontrolled extension (Trial 9) in 82 pediatric patients 10 years of age and older with type 2 diabetes, a pediatric pharmacokinetic study, and studies in adults with type 2 diabetes mellitus [see Clinical Pharmacology (12.3) and Clinical Studies (14.2, 14.3, 14.4, 14.6)].

Safety and effectiveness of BYDUREON BCISE have not been established in pediatric patients less than 10 years of age.

8.5 Geriatric Use

In two comparator-controlled 28-week trials, BYDUREON BCISE was studied in 74 patients (18%) who were at least 65 years of age and 10 (2.4%) patients who were at least 75 years of age. In these studies, no meaningful differences in safety and effectiveness were observed between patients ≥65 years of age and younger adult patients, but these studies did not include sufficient numbers of patients ≥75 years of age to determine whether they respond differently from younger adult patients.

In a large cardiovascular outcomes trial [see Clinical Studies (14.5)], BYDUREON was studied in 2,959 patients (40%) who were at least 65 years old and of those, 605 patients (8%) were at least 75 years old.

Use caution when initiating BYDUREON BCISE in geriatric patients because they are more likely to have decreased kidney function [see Use in Specific Populations (8.6)].

8.6 Renal Impairment

Pharmacokinetic studies of adult patients with renal impairment who received BYDUREON BCISE indicate that there is an increase in exenatide exposure in those with mild and moderate renal impairment as compared to patients with normal kidney function. BYDUREON BCISE may induce nausea and vomiting with transient hypovolemia and may worsen kidney function in patients with renal impairment.

Monitor patients with mild renal impairment for adverse reactions that may lead to hypovolemia. BYDUREON BCISE is not recommended for use in patients with eGFR below 45 mL/min/1.73 m^2 or end-stage renal disease. If BYDUREON BCISE is used in patients with renal transplantation, closely monitor for adverse reactions that may lead to hypovolemia [see Warnings and Precautions (5.4) and Clinical Pharmacology (12.3)].

10 OVERDOSAGE

Effects of overdoses with BYETTA, another exenatide product, included severe nausea, severe vomiting, and rapidly declining blood glucose concentrations, including severe hypoglycemia requiring parenteral glucose administration. In the event of overdose, consider contacting the Poison Help line (1-800-222-1222) or a medical toxicologist for additional overdosage management recommendations. Initiate appropriate supportive treatment according to the patient's clinical signs and symptoms.

11 DESCRIPTION

BYDUREON BCISE (exenatide) extended-release injectable suspension is a GLP-1 receptor agonist supplied as a sterile suspension of exenatide extended-release microspheres in an oil-based vehicle of medium chain triglycerides (MCT), in a single-dose autoinjector. Redispersion by mixing provides a white to off-white, opaque, suspension to be administered by subcutaneous injection. Each autoinjector contains sufficient suspension to deliver 2 mg of exenatide extended-release in a volume of 0.85 mL.

Exenatide is a 39-amino acid synthetic peptide amide with an empirical formula of C184H282N50O60S and a molecular weight of 4186.6 Daltons. The amino acid sequence for exenatide is shown below.

H-His-Gly-Glu-Gly-Thr-Phe-Thr-Ser-Asp-Leu-Ser-Lys-Gln-Met-Glu-Glu-Glu-Ala-Val-Arg-Leu-Phe-Ile-Glu-Trp-Leu-Lys-Asn-Gly-Gly-Pro-Ser-Ser-Gly-Ala-Pro-Pro-Pro-Ser-NH2

Exenatide is incorporated in an extended-release microsphere formulation containing the 50:50 poly (D,L-lactide-co-glycolide) polymer (37.2 mg per dose) along with sucrose (0.8 mg per dose), suspended in the vehicle, MCT (774.4 mg per dose).

12 CLINICAL PHARMACOLOGY

12.1 Mechanism of Action

Incretins, such as GLP-1, enhance glucose-dependent insulin secretion and exhibit other antihyperglycemic actions following their release into the circulation from the gut. Exenatide is a GLP-1 receptor agonist that enhances glucose-dependent insulin secretion by the pancreatic beta-cell, suppresses inappropriately elevated glucagon secretion, and slows gastric emptying.

The amino acid sequence of exenatide partially overlaps that of human GLP-1. Exenatide is a GLP-1 receptor agonist that has been shown to bind and activate the human GLP-1 receptor in vitro. This leads to an increase in both glucose-dependent synthesis of insulin and in vivo secretion of insulin from pancreatic beta-cells, by mechanisms involving cyclic AMP and/or other intracellular signaling pathways. Exenatide promotes insulin release from pancreatic beta-cells in the presence of elevated glucose concentrations.

12.2 Pharmacodynamics

Exenatide improves glycemic control through the actions described below.

Glucose-Dependent Insulin Secretion

The effect of exenatide infusion on glucose-dependent insulin secretion rates (ISR) was investigated in 11 healthy subjects. In these healthy subjects, on average, the ISR response was glucose-dependent (Figure 1). Exenatide did not impair the normal glucagon response to hypoglycemia.

Figure 1: Mean (SE) Insulin Secretion Rates During Infusion of Exenatide or Placebo by Treatment, Time, and Glycemic Condition in Healthy Subjects

SE = standard error.
Notes: 5 mmol = 90 mg/dL, 4 mmol/L = 72 mg/dL, 3.2 mmol/L = 58 mg/dL; Study medication infusion was started at time = 0 minutes.
Statistical assessments were for the last 30 minutes of each glycemic step, during which the target glucose concentrations were maintained.
*p <0.05, exenatide treatment relative to placebo.

Glucagon Secretion

In patients with type 2 diabetes, exenatide moderates glucagon secretion and lowers serum glucagon concentrations during periods of hyperglycemia.

Gastric Emptying

Exenatide slows gastric emptying, thereby reducing the rate at which postprandial glucose appears in the circulation.

Fasting and Postprandial Glucose

In a 12-week clinical pharmacology study of exenatide microspheres suspended in MCT-oil in adults with type 2 diabetes mellitus, reductions in fasting plasma glucose were evident after 2 weeks of treatment, and after 12 weeks resulted in a reduction of fasting plasma glucose concentrations of -40.4 mg/dL, when compared to placebo.

In a clinical study of BYDUREON BCISE, 2‑hour postprandial glucose levels were measured at Week 16, during a mixed meal tolerance test, in a subset of patients with type 2 diabetes mellitus. The mean change from baseline was −78 mg/dL.

Cardiac Electrophysiology

The effect of exenatide at therapeutic (253 pg/mL) and supratherapeutic (627 pg/mL) concentrations, following an intravenous infusion on QTc interval was evaluated in a randomized, placebo- and active-controlled (moxifloxacin 400 mg) three-period crossover thorough QT study in 74 healthy subjects. The upper bound of the one-sided 95% confidence interval for the largest placebo adjusted, baseline-corrected QTc based on population correction method (QTcP) was below 10 ms. Therefore, exenatide was not associated with prolongation of the QTc interval at therapeutic and supratherapeutic concentrations.

12.3 Pharmacokinetics

Absorption

Following a single subcutaneous dose of exenatide microspheres suspended in MCT-oil, there is an initial period of release of surface-bound exenatide followed by a gradual release of exenatide from the microspheres, which results in a peak of plasma exenatide concentration at around Week 6 to Week 7 representing the hydration and erosion of the microspheres.

Following initiation of once every 7 days (weekly) administration of 2 mg BYDUREON BCISE, a gradual increase in the plasma exenatide concentration is observed up to approximately Week 10. From Week 10 mean plasma exenatide concentrations of approximately 208 pg/mL were maintained over once every 7 days (weekly) dosing intervals indicating that steady-state was achieved.

Distribution

The mean apparent volume of distribution of exenatide following subcutaneous administration of a single-dose of BYETTA is 28.3 L and is expected to remain unchanged for BYDUREON BCISE.

Metabolism

Elimination

Nonclinical studies have shown that exenatide is predominantly eliminated by glomerular filtration with subsequent proteolytic degradation. The mean apparent clearance of exenatide in humans is 9.1 L/hour and is independent of the dose. Approximately 10 weeks after discontinuation of BYDUREON BCISE therapy, plasma exenatide concentrations generally fall below the minimal quantifiable concentration of 20 pg/mL.

Specific Populations

Patients with Renal Impairment

BYDUREON BCISE has not been studied in patients with severe renal impairment (CrCL <30 mL/min, eGFR <30 mL/min/1.73m^2) or end-stage renal disease receiving dialysis. Pharmacokinetic analysis of patients receiving 2 mg BYDUREON BCISE indicated that there was a 28% and 69% higher systemic exposure to exenatide in patients with mild (N=96) or moderate (N=24) renal impairment, respectively, as compared to patients with normal renal function (N=70) [see Warnings and Precautions (5.4) and Use in Specific Populations (8.6)]. In a study of BYETTA in subjects with end-stage renal disease receiving dialysis, mean exenatide exposure increased by 3.4-fold compared to that of subjects with normal renal function [see Warnings and Precautions (5.4) and Use in Specific Populations (8.6)].

Patients with Hepatic Impairment

BYDUREON BCISE has not been studied in patients with acute or chronic hepatic impairment.

Age, Male and Female Patients, Race or Ethnic Groups, and Body Weight

Age, gender, race and body weight did not alter the pharmacokinetics of BYDUREON BCISE in population pharmacokinetic analyses.

Pediatric Patients

The pharmacokinetics of BYDUREON BCISE has not been studied in pediatric patients [see Use in Specific Populations (8.4)]. The clinical pharmacology of BYDUREON, another formulation of exenatide extended-release, has been evaluated in the population pharmacokinetic study in adolescent patients with type 2 diabetes mellitus between age 11 and age less than 18 years old. The pharmacokinetic profile of BYDUREON in the pediatric population is consistent with that of BYDUREON and BYDUREON BCISE in adults. The pharmacokinetic behavior of BYDUREON BCISE is expected to be consistent with that of BYDUREON in adolescent patients.

Drug Interaction Studies The following drug interactions have been studied using BYDUREON. The potential for drug-drug interaction with BYDUREON BCISE is expected to be similar to that of BYDUREON.

Acetaminophen

When 1000 mg acetaminophen tablets were administered, either with or without a meal, following 14 weeks of BYDUREON therapy (2 mg weekly), no significant changes in acetaminophen AUC were observed compared to the control period. Acetaminophen Cmax decreased by 16% (fasting) and 5% (fed) and Tmax was increased from approximately 1 hour in the control period to 1.4 hours (fasting) and 1.3 hours (fed).

The following drug interactions have been studied using BYETTA. The potential for drug-drug interaction with BYDUREON BCISE is expected to be similar to that of BYETTA.

Warfarin

Administration of warfarin (25 mg) 35 minutes after repeated doses of BYETTA (5 mcg twice daily on days 1-2 and 10 mcg twice daily on days 3-9) in healthy volunteers delayed warfarin Tmax by approximately 2 hours. No clinically relevant effects on Cmax or AUC of S- and R-enantiomers of warfarin were observed. BYETTA did not significantly alter the pharmacodynamic properties (e.g., international normalized ratio) of warfarin [see Drug Interactions (7)].

Digoxin

Administration of repeated doses of BYETTA 30 minutes before oral digoxin (0.25 mg once daily) decreased the Cmax of digoxin by 17% and delayed the Tmax of digoxin by approximately 2.5 hours; however, the overall steady-state pharmacokinetic exposure (e.g., AUC) of digoxin was not changed.

Lovastatin

Administration of BYETTA (10 mcg twice daily) 30 minutes before a single oral dose of lovastatin (40 mg) decreased the AUC and Cmax of lovastatin by approximately 40% and 28%, respectively, and delayed the Tmax by about 4 hours compared with lovastatin administered alone. In the 30-week controlled clinical trials of BYETTA, the use of BYETTA in patients already receiving HMG CoA reductase inhibitors was not associated with consistent changes in lipid profiles compared to baseline.

Lisinopril

In patients with mild to moderate hypertension stabilized on lisinopril (5-20 mg/day), BYETTA (10 mcg twice daily) did not alter steady-state Cmax or AUC of lisinopril. Lisinopril steady-state Tmax was delayed by 2 hours. There were no changes in 24-hour mean systolic and diastolic blood pressure.

Oral Contraceptives

The effect of BYETTA (10 mcg twice daily) on single and on multiple doses of a combination oral contraceptive (30 mcg ethinyl estradiol plus 150 mcg levonorgestrel) was studied in healthy female subjects. Repeated daily doses of the oral contraceptive (OC) given 30 minutes after BYETTA administration decreased the Cmax of ethinyl estradiol and levonorgestrel by 45% and 27%, respectively, and delayed the Tmax of ethinyl estradiol and levonorgestrel by 3.0 hours and 3.5 hours, respectively, as compared to the oral contraceptive administered alone. Administration of repeated daily doses of the OC one hour prior to BYETTA administration decreased the mean Cmax of ethinyl estradiol by 15%, but the mean Cmax of levonorgestrel was not significantly changed as compared to when the OC was given alone. BYETTA did not alter the mean trough concentrations of levonorgestrel after repeated daily dosing of the oral contraceptive for both regimens. However, the mean trough concentration of ethinyl estradiol was increased by 20% when the OC was administered 30 minutes after BYETTA administration injection as compared to when the OC was given alone. The effect of BYETTA on OC pharmacokinetics is confounded by the possible food effect on OC in this study [see Drug Interactions (7)].

12.6 Immunogenicity

The observed incidence of anti-drug antibodies is highly dependent on the sensitivity and specificity of the assay. Differences in assay methods preclude meaningful comparisons of the incidence of anti-drug antibodies in the studies described below with the incidence of anti-drug antibodies in other studies, including those of BYDUREON BCISE or of other exenatide products.

Immunogenicity of BYDUREON BCISE in Adult Patients

Anti-exenatide antibodies were measured at prespecified intervals in the two controlled studies of BYDUREON BCISE in adults with type 2 diabetes mellitus (Trials 1 and 2) [see Clinical Studies (14.2)]. During the 28-week treatment period in these trials, 125/393 (32%) of the BYDUREON BCISE-treated patients with evaluable anti-exenatide antibody measurements developed high titer antibodies (high titer was defined as ≥625). BYDUREON BCISE-treated patients that had higher titer antibodies had a lower glycemic response compared to BYDUREON BCISE-treated patients who did not have anti-exenatide antibodies during the treatment period [see Warnings and Precautions (5.6)]. The percentage of BYDUREON BCISE-treated patients with positive antibody titers peaked at approximately Weeks 8-16 of dosing.

Amongst BYDUREON BCISE-treated patients evaluable for anti-exenatide antibodies (N=393), injection site reactions were more commonly observed in those with high titer anti-exenatide antibodies (≥625) compared to those with low titer anti-exenatide antibodies (<625) or those who did not develop anti-exenatide antibodies [see Adverse Reactions (6.1)]. There is insufficient data to assess whether the observed anti-exenatide antibodies in adult patients had an effect on the severity of injection site reactions, or on the incidence or severity of hypersensitivity reactions.

A total of 118 adult patients with high titer anti-exenatide antibodies in BYDUREON BCISE trials were tested for the presence of cross-reactive antibodies to GLP-1 and/or glucagon and one patient (0.8%) developed cross-reactive antibodies to GLP-1 and/or glucagon.

Immunogenicity of BYDUREON in Pediatric Patients

In a 52-week BYDUREON trial (24-week controlled and 28-week extended treatment period) for the improvement of glycemic control in pediatric patients with type 2 diabetes mellitus (Trial 9) [see Clinical Studies (14.6)], 37/58 (64%) of BYDUREON-treated patients had high titer anti-exenatide antibodies (high titer was defined as ≥625) at any time during the study. In this trial, 60% of these patients had a peak high-titers at approximately Week 12. BYDUREON-treated pediatric patients that had high titer anti-exenatide antibodies appeared to have had a lower glycemic response compared to BYDUREON-treated pediatric patients who did not have anti-exenatide antibodies during this trial [see Warnings and Precautions (5.6)].

There is insufficient data to assess whether the observed anti-exenatide antibodies in pediatric patients had an effect on the incidence or severity of hypersensitivity reactions or injection site reactions.

The potential for development of antibodies cross-reactive with endogenous GLP-1 and glucagon has not been evaluated in BYDUREON-treated pediatric patients.

Anti-Drug Antibody Effects on Pharmacokinetics in Adult and Pediatric Patients

The percentage of exenatide-treated adult and pediatric patients (age ≥11 years) with high anti-exenatide antibody titers (≥625) that had steady state exenatide plasma concentrations below limit of quantitation was higher than in those with low anti-exenatide antibody titers (<625).

13 NONCLINICAL TOXICOLOGY

13.1 Carcinogenesis, Mutagenesis, Impairment of Fertility

Thyroid C-cell tumors have been observed in rats and mice with GLP-1 receptor agonists.

A 2‑year carcinogenicity study was conducted with exenatide extended-release, the active component of BYDUREON BCISE, in male and female rats at doses of 0.3, 1.0, and 3.0 mg/kg (2-, 10-, and 27-times human systemic exposure at the maximum recommended human dose (MRHD) of 2 mg/week. BYDUREON BCISE based on plasma exenatide AUC, respectively) administered by subcutaneous injection every other week. In this study there was an increased incidence of C-cell adenomas and C-cell carcinomas at all doses. An increase in benign fibromas was seen in the skin subcutis at injection sites of males given 3 mg/kg. No treatment-related injection-site fibrosarcomas were observed at any dose. The human relevance of these findings is currently unknown.

Carcinogenicity of exenatide extended-release has not been evaluated in mice.

Exenatide, the active ingredient in BYDUREON BCISE, was not mutagenic or clastogenic, with or without metabolic activation, in the Ames bacterial mutagenicity assay or chromosomal aberration assay in Chinese hamster ovary cells. Exenatide was negative in the in vivo mouse micronucleus assay.

In mouse fertility studies with exenatide, the active ingredient in BYDUREON BCISE, at twice-daily subcutaneous doses of 6, 68, or 760 mcg/kg/day, males were treated for 4 weeks prior to and throughout mating, and females were treated 2 weeks prior to mating and throughout mating until gestation day 7. No adverse effect on fertility was observed at 760 mcg/kg/day, a systemic exposure 163-times the human exposure resulting from the recommended dose of 2 mg/week, based on AUC.

14 CLINICAL STUDIES

14.1 Overview of Clinical Studies

BYDUREON BCISE has been studied in adult patients with type 2 diabetes mellitus as monotherapy and in combination with metformin, a sulfonylurea, a thiazolidinedione, a combination of metformin and a sulfonylurea, or a combination of metformin and a thiazolidinedione [see Clinical Studies (14.2)].

The effectiveness of BYDUREON BCISE as an adjunct to diet and exercise to improve glycemic control in adults and pediatric patients aged 10 years and older with type 2 diabetes mellitus was also supported by adequate and well-controlled studies of BYDUREON, another extended-release exenatide product, in adult and pediatric patients aged 10 years and older with type 2 diabetes mellitus [see Clinical Studies (14.3, 14.4, 14.6)].

Cardiovascular (CV) outcomes were studied in the EXSCEL trial that enrolled adult patients with type 2 diabetes mellitus and multiple risk factors for CV disease or established CV disease [see Clinical Studies (14.5)].

14.2 BYDUREON BCISE Glycemic Control Trials in Adults with Type 2 Diabetes Mellitus

BYDUREON BCISE versus BYETTA, Both as Monotherapy or as Add-on to Metformin, a Sulfonylurea, a Thiazolidinedione, or Combination of Oral Agents

A 28-week, randomized, open-label comparator-controlled trial was conducted to compare the safety and efficacy of BYDUREON BCISE to BYETTA in adult patients with type 2 diabetes and inadequate glycemic control with diet and exercise alone or with oral antidiabetic therapy, including metformin, a sulfonylurea, a thiazolidinedione, or a combination of any two of these therapies (Trial 1 - NCT01652716). Patients were randomly assigned to receive BYDUREON BCISE 2 mg given subcutaneously once every 7 days (weekly) (n=229) or BYETTA (10 mcg twice daily) (n=146), in addition to existing oral antidiabetic agents. Patients assigned to BYETTA initiated treatment with 5 mcg twice daily then increased the dosage to 10 mcg twice daily after 4 weeks.

A total of 375 adult patients were studied: 278 (74%) were White, 61 (16%) were Black or African American, 25 (7%) were of Asian ethnicity, 5 (1%) were listed as other, 5 (1%) were American Indian or Alaska Native, and 1 (<1%) was Native Hawaiian or Other Pacific Islander. Patients were treated with diet and exercise alone (13%), a single oral antidiabetic agent (49%), or combination therapy of oral antidiabetic agents (38%). The mean baseline HbA1c was 8.5%. The primary endpoint was change in HbA1c from baseline to Week 28.

Efficacy Results:

The results for the primary endpoint at Week 28 are summarized in Table 4. Treatment with BYDUREON BCISE 2 mg once weekly (QW) resulted in a statistically significantly greater reduction in HbA1c compared to BYETTA 10 mcg twice daily. The mean reduction in HbA1c was non-inferior compared with BYETTA 10 mcg twice daily at the pre-specified non-inferiority margin +0.4% in this study. BYDUREON BCISE 2 mg QW was statistically superior to BYETTA 10 mcg twice daily (ANCOVA p-value=0.0032).

The proportions of subjects achieving HbA1c <7.0% at Week 28 were 40% in BYDUREON BCISE group compared to 38% in BYETTA group. Subjects with missing values at Week 28 counted as non-responders. The mean changes from baseline to Week 28 for fasting plasma glucose were -36 mg/dL and -27 mg/dL for BYDUREON BCISE and BYETTA, respectively, and for body weight were -1.4 kg and -1.9 kg for BYDUREON BCISE and BYETTA, respectively.

Table 4: Results of 28-Week Trial of BYDUREON BCISE versus BYETTA, Both as Monotherapy or as Add-On to Metformin, a Sulfonylurea, a Thiazolidinedione, or Combination of Oral Agents in Patients with Type 2 Diabetes Mellitus (Trial 1)
 | BYDUREON BCISE 2 mg QW | BYETTA 10 mcg twice daily [Least squares means were obtained using an Analysis of Covariance (ANCOVA) model with treatment, baseline HbA1c, baseline HbA1c stratum (<9% or ≥9%), diabetes management method at screening (diet/exercise alone, SU use, or non-SU use), and renal function (normal, mild, or moderate renal impairment) in the population included subjects discontinued treatment before 28 weeks regardless of initiation of rescue medicine.]
Intent-to-Treat Population (N) | 229 | 146
HbA1c (%)
Mean Baseline | 8.5 | 8.5
Mean Change at Week 28 | ‑1.39 | ‑1.03
Difference from BYETTA[95% CI] | ‑0.36 [p-value <0.01]; (‑0.66, ‑0.14)
N = number of patients in each treatment group, CI = unadjusted confidence interval, QW = once weekly.

BYDUREON BCISE versus Sitagliptin and Placebo, All as Add-on to Metformin Therapy

A 28-week open-label (oral medication blinded), comparator- and placebo-controlled trial was conducted to compare the safety and efficacy of BYDUREON BCISE to sitagliptin and placebo in adult patients with type 2 diabetes whose glycemic control was inadequate with metformin therapy (Trial 2 - NCT01652729). Patients were randomly assigned to receive BYDUREON BCISE 2 mg given subcutaneously once every 7 days (weekly) (n=181), sitagliptin 100 mg/day (n=122) or placebo (n=61), in addition to their existing metformin therapy.

A total of 364 adult patients were studied, 296 (81%) were White, 49 (14%) Black or African American, 14 (4%) Asian and 3 (<1%) American Indian or Alaska Native, 1 (<1%) Native Hawaiian or Other Pacific Islander, and 1 (<1%) was classified otherwise. The mean baseline HbA1c was 8.5%.

The primary endpoint was change in HbA1c from baseline to Week 28.

Efficacy Results:

Results for the primary endpoint at 28 weeks are summarized in Table 5. In this study, treatment with BYDUREON BCISE 2 mg once weekly resulted in a statistically significant mean reduction in HbA1c compared to placebo. BYDUREON BCISE 2 mg was statistically superior to placebo (ANCOVA p-value=0.02).

The proportions of subjects who achieved an HbA1c <7.0% at Week 28 were 41%, 31%, and 26% in BYDUREON BCISE, Sitagliptin and Placebo groups, respectively. Subjects with missing values at Week 28 counted as non-responders. The mean changes from baseline to Week 28 for fasting plasma glucose were -24 mg/dL, -19 mg/dL and -1 mg/dL for BYDUREON BCISE, Sitagliptin and Placebo, respectively, and for body weight were -1.4 kg, -1.2 kg, and 0.4 kg for BYDUREON BCISE, Sitagliptin and Placebo, respectively.

Table 5: Results of 28-Week Trial of BYDUREON BCISE versus Sitagliptin and Placebo, All as Add-On to Metformin Therapy in Adult Patients with Type 2 Diabetes Mellitus (Trial 2)
 | BYDUREON BCISE 2 mg QW | Sitagliptin 100 mg/day | Placebo once daily
Intent-to-Treat Population (N) | 181 | 122 | 61
HbA1c (%)
Mean Baseline | 8.4 | 8.5 | 8.5
Mean Change at Week 28 | ‑1.07 | ‑0.79 | ‑0.59
Difference from sitagliptin [Least squares means were obtained using an Analysis of Covariance (ANCOVA) model with treatment, baseline HbA1c and baseline HbA1c stratum (<9% or ≥ 9%) in the population included subjects discontinued treatment before 28 weeks regardless of initiation of rescue medicine.] [Sitagliptin 100 mg/day did not show the superiority to placebo in this study.] [95% CI] | ‑0.28; (‑0.62, 0.02)
Difference from placebo [95% CI] | ‑0.49; (‑0.91, ‑0.07) [p-value <0.05]
N = number of patients in each treatment group, CI = unadjusted confidence interval, QW = once weekly.

14.3 BYDUREON Glycemic Control Trials in Adults with Type 2 Diabetes Mellitus - Monotherapy

BYDUREON, another exenatide extended-release product, has been studied as monotherapy in adult patients with type 2 diabetes mellitus.

BYDUREON Monotherapy versus Metformin, Sitagliptin, and Pioglitazone

A 26-week, randomized, comparator-controlled trial was conducted to compare the safety and efficacy of BYDUREON to metformin, sitagliptin, and pioglitazone in patients with type 2 diabetes whose glycemic control was inadequate with diet and exercise (Trial 3 - NCT00676338). Patients were randomly assigned to receive BYDUREON 2 mg given subcutaneously once every seven days (weekly), titrated metformin from 1000 to 2500 mg/day, sitagliptin 100 mg/day or titrated pioglitazone from 30 to 45 mg/day, all dosed according to approved labeling.

A total of 820 patients were studied: 552 (67%) were White, 102 (12%) were East Asian, 71 (9%) were West Asian, 65 (8%) were Hispanic or Latino, 25 (3.0%) were Black or African American, 4 (0.5%) were of Native American ethnicity, and 1 was classified otherwise. The mean baseline HbA1c was 8.5%.

The primary endpoint was change in HbA1c from baseline to Week 26 (or the last value at time of early discontinuation).

Efficacy Results:

Treatment with BYDUREON 2 mg once weekly (QW) resulted in mean HbA1c reduction that was statistically significantly greater compared to sitagliptin 100 mg/day. The mean reduction in HbA1c was non-inferior compared with metformin 1000-2500 mg/day (mean dose 2077 mg/day at study endpoint). Non-inferiority of BYDUREON 2 mg QW to pioglitazone 30-45 mg/day (mean dose 40 mg/day at study endpoint) in reducing HbA1c after 26 weeks of treatment was not demonstrated (the mean change from baseline in HbA1c after 26 weeks was -1.6% with BYDUREON and -1.7% with pioglitazone). The non-inferiority margin was set at +0.3% in this study. The results for the primary endpoint at 26 weeks are summarized in Table 6.

The proportion of patients with a Week 26 value achieving HbA1c of less than 7% at Week 26 were 56%, 52%, 40%, and 55% for BYDUREON, metformin, sitagliptin, and pioglitazone, respectively. Patients who did achieve HbA1c goal <7% and discontinued before Week 26 were not included as responders. The mean changes from baseline to Week 26 for fasting serum glucose were -41 mg/dL, -36 mg/dL, -20 mg/dL and -46 mg/dL, and for body weight were -2.0 kg, -2.0 kg, -0.8 kg and +1.5 kg for BYDUREON, metformin, sitagliptin, and pioglitazone, respectively.

Table 6: Results of 26-Week Trial of BYDUREON Monotherapy versus Metformin, Sitagliptin, and Pioglitazone in Patients with Type 2 Diabetes Mellitus (Trial 3)
 | BYDUREON 2 mg QW | Metformin 1000-2500 (mean dose 2077) mg/day | Sitagliptin 100 mg/day | Pioglitazone 30-45 (mean dose 40) mg/day
Intent-to-Treat Population (N) | 248 | 246 | 163 | 163
HbA1c (%)
Mean Baseline | 8.4 | 8.6 | 8.4 | 8.5
Mean Change at Week 26 [Least squares means were obtained using a mixed model repeated measure analysis with treatment, pooled country, visit, baseline HbA1c value, and treatment by visit interaction as fixed effects, and subject as a random effect.] | −1.6 | −1.5 | −1.2 | −1.7
Difference from metformin [Bonferroni-adjusted 98.3% CI] | −0.05 [−0.26, 0.17]
Difference from sitagliptin [Bonferroni-adjusted 98.3% CI] | −0.39 [p<0.001, treatment vs comparator.] [−0.63, −0.16]
Difference from pioglitazone [Bonferroni-adjusted 98.3% CI] | 0.16 [−0.08, 0.41]
N = number of patients in each treatment group; mean change is least squares mean change; QW = once weekly.
The primary efficacy analysis was adjusted for multiple comparisons and a two-sided 98.3% confidence interval was utilized to assess difference between treatments.
HbA1c change data at 26 weeks were available from 86%, 87%, 85%, and 82% of the randomized subjects in the BYDUREON, metformin, sitagliptin, and pioglitazone groups, respectively.

14.4 BYDUREON Glycemic Control Trials in Adults with Type 2 Diabetes Mellitus - Combination Therapy

BYDUREON, another exenatide extended-release product, has been studied in combination with metformin, sulfonylurea, thiazolidinedione, sodium-glucose cotransporter-2 (SGLT2) inhibitor and basal insulin in adult patients with type 2 diabetes mellitus.

BYDUREON versus Sitagliptin and Pioglitazone, All as Add-on to Metformin Therapy

A 26-week double-blind comparator-controlled trial was conducted to compare the safety and efficacy of BYDUREON to sitagliptin and pioglitazone in patients with type 2 diabetes whose glycemic control was inadequate with metformin therapy (Trial 4 - NCT00637273). Patients were randomly assigned to receive BYDUREON 2 mg given subcutaneously once every 7 days (weekly), sitagliptin 100 mg/day or pioglitazone 45 mg/day, in addition to their existing metformin therapy.

A total of 491 patients were studied 168 (34.2%) were White, 143 (29.1%) were Hispanic or Latino, 119 (24.2%) were Asian, 52 (10.6%) were Black or African American, 3 (0.6%) were of Native American ethnicity, and 6 (1.2%) were classified otherwise. The mean baseline HbA1c was 8.5%.

The primary endpoint was change in HbA1c from baseline to Week 26 (or the last value at time of early discontinuation).

Efficacy Results:

In this study, treatment with BYDUREON 2 mg QW resulted in a statistically significant mean HbA1c reduction compared to sitagliptin 100 mg/day. There was a numerically greater reduction in HbA1c with BYDUREON compared to pioglitazone, but there was not sufficient evidence to conclude superiority of BYDUREON 2 mg QW to pioglitazone 45 mg/day in reducing HbA1c after 26 Weeks of treatment. Results for the primary endpoint at 26 Weeks are summarized in Table 7.

The proportion of patients with a Week 26 value achieving HbA1c of less than 7% at Week 26 were 46%, 30%, and 39% for BYDUREON, sitagliptin, and pioglitazone, respectively. Patients who did achieve an HbA1c goal <7% and discontinued before Week 26 were not included as responders. The mean changes from baseline to Week 26 for fasting serum glucose were -32 mg/dL, -16 mg/dL and -27 mg/dL, and for body weight were -2.3 kg, -0.8 kg and +2.8 kg for BYDUREON, sitagliptin, and pioglitazone, respectively.

Table 7: Results of 26-Week Trial of BYDUREON versus Sitagliptin and Pioglitazone, All as Add-On to Metformin Therapy in Patients with Type 2 Diabetes Mellitus (Trial 4)
 |  | BYDUREON 2 mg QW | Sitagliptin 100 mg/day | Pioglitazone 45 mg/day
Intent-to-Treat Population (N) |  | 160 | 166 | 165
 | HbA1c (%)
Mean Baseline |  | 8.6 | 8.5 | 8.5
Mean Change at Week 26 [Least squares means were obtained using an ANCOVA model with treatment, baseline HbA1c stratum, and country as fixed effects. Missing Week 26 data (28%, 18%, and 24% for the BYDUREON, sitagliptin, and pioglitazone groups, respectively) were imputed by the LOCF technique.] |  | −1.5 | −0.9 | −1.2
Difference from sitagliptin [95% CI] |  | −0.63; [−0.89, −0.37]
Difference from pioglitazone; [95% CI] |  | −0.32; [−0.57, −0.06]
N = number of patients in each treatment group; mean change is least squares mean change; QW = once weekly. QW = once weekly.

BYDUREON versus Insulin Glargine, Both as Add-on to Metformin or Metformin + Sulfonylurea Therapy

A 26-week open-label comparator-controlled trial was conducted to compare the safety and efficacy of BYDUREON to titrated insulin glargine in patients with type 2 diabetes whose glycemic control was inadequate with metformin or metformin plus sulfonylurea therapy (Trial 5 - NCT00641056). Patients were randomly assigned to receive BYDUREON 2 mg given subcutaneously once every 7 days (weekly) or insulin glargine once daily in addition to their existing oral antidiabetic therapy. Insulin glargine was dosed to a target fasting glucose concentration of 72 to 100 mg/dL.

The mean dose of insulin glargine was 10 units/day at baseline and 31 units/day at endpoint. At Week 26, 21% of insulin glargine-treated patients were at fasting glucose goal.

A total of 456 patients were studied: 379 (83.1%) were White, 47 (10.3%) were Hispanic or Latino, 25 (5.5%) were East Asian, 3 (0.7%) were Black or African American, and 2 (0.4%) were of West Asian ethnicity. Background therapy was either metformin (70%) or metformin plus sulfonylurea (30%). The mean baseline HbA1c was 8.3%.

The primary endpoint was change in HbA1c from baseline to Week 26 (or the last value at time of early discontinuation).

Efficacy Results:

Treatment with BYDUREON once weekly resulted in a mean reduction in HbA1c from baseline at 26 weeks of -1.5%. The mean reduction in HbA1c seen in insulin glargine arm at 26 weeks was -1.3%. The difference in observed effect size between BYDUREON and glargine in this trial excluded the pre-specified non-inferiority margin of +0.3%.

The proportion of patients with a Week 26 value achieving HbA1c of less than 7% at Week 26 were 57% and 48% for BYDUREON and insulin glargine, respectively. Patients who did achieve an HbA1c goal <7% and discontinued before Week 26 were not included as responders. The mean changes from baseline to Week 26 for fasting serum glucose in this study were -38 mg/dL and -50 mg/dL, and for body weight were -2.6 kg and +1.4 kg for BYDUREON and insulin glargine, respectively.

BYDUREON versus Liraglutide, Both as Add-on to Metformin, a Sulfonylurea, Metformin + Sulfonylurea, or Metformin + Pioglitazone Therapy

A 26-week open-label comparator-controlled trial was conducted to compare the safety and efficacy of BYDUREON to liraglutide in patients with type 2 diabetes whose glycemic control was inadequate with metformin, a sulfonylurea, metformin plus sulfonylurea, or metformin plus pioglitazone therapy (Trial 6 - NCT01029886). Patients were randomly assigned to receive BYDUREON 2 mg given subcutaneously once every 7 days (weekly) or liraglutide uptitrated from 0.6 mg/day to 1.2 mg/day, then 1.8 mg/day in addition to their existing oral antidiabetic therapy. Each titration was to be completed after at least one week, but could be delayed if the patient had severe nausea or vomiting as established by the investigator. Patients not tolerating the 1.8 mg/day dose of liraglutide by Week 4 were discontinued from the study.

A total of 911 patients were studied: 753 (82.7%) were White, 111 (12.2%) were Asian, 32 (3.5%) were American Indian or Alaska Native, 8 (0.9%) were of Black or African American ethnicity, 6 (0.7%) were multiple races, and 1 (0.1%) was Pacific Islander. Background therapy was either a single oral antidiabetic agent (35%) or a combination of oral antidiabetic agents (65%). The mean baseline HbA1c was 8.4%.

The primary endpoint was change in HbA1c from baseline to Week 26 (or the last value at time of early discontinuation).

Efficacy Results:

Treatment with BYDUREON once weekly resulted in a mean reduction in HbA1c from baseline at 26 weeks of -1.3%. The mean reduction in HbA1c seen in the liraglutide arm at 26 weeks was -1.5%. The HbA1c reduction with BYDUREON did not meet predefined non-inferiority criteria compared to liraglutide 1.8 mg/day. The non-inferiority margin was set at +0.25% in this study. Results for the primary endpoint at 26 weeks are summarized in Table 8.

The proportion of patients with a Week 26 value achieving HbA1c of less than 7% at Week 26 were 48% and 56% for BYDUREON and liraglutide, respectively. Patients who did achieve an HbA1c goal <7% and discontinued before Week 26 were not included as responders. The mean changes from baseline to Week 26 for fasting serum glucose were -32 mg/dL and -38 mg/dL, and for body weight were -2.7 kg and -3.6 kg for BYDUREON and liraglutide, respectively.

Table 8: Results of 26-Week Trial of BYDUREON versus Liraglutide, Both as Add-On to Metformin, a Sulfonylurea, Metformin + Sulfonylurea, or Metformin + Pioglitazone Therapy in Patients with Type 2 Diabetes Mellitus (Trial 6)
 | BYDUREON 2 mg QW | Liraglutide 1.8 mg/day
Intent-to-Treat Population (N) | 461 | 450
HbA1c (%)
Mean Baseline | 8.5 | 8.4
Mean Change at Week 26 [Least squares means were obtained using a mixed model repeated measure analysis with treatment, country, OAD stratum, baseline HbA1c stratum, visit, baseline HbA1c and treatment by visit interaction as fixed effects, and subject as a random effect.] | −1.3 | −1.5
Difference from liraglutide [95% CI] | 0.2 [0.08, 0.33]
N = number of patients in each treatment group; mean change is least squares mean change; QW = once weekly.
HbA1c change data at 26 weeks were available from 85% and 86% of the randomized subjects in the BYDUREON and liraglutide groups, respectively.

BYDUREON in Combination with Dapagliflozin versus BYDUREON Alone and Dapagliflozin Alone, All as Add-On to Metformin

A 28-week double-blind comparator-controlled trial was conducted to compare the efficacy of BYDUREON and dapagliflozin (an SGLT2 inhibitor) to BYDUREON alone and dapagliflozin alone in patients with type 2 diabetes with inadequate glycemic control with metformin therapy (Trial 7 - NCT02229396). All patients entered a 1- week placebo lead–in period. Patients with HbA1c ≥8.0% and ≤12% and on metformin at a dose of at least 1,500 mg per day were randomly assigned to receive either BYDUREON 2 mg given subcutaneously once every 7 days (weekly) plus dapagliflozin 10 mg once daily, BYDUREON 2 mg given subcutaneously once weekly, or dapagliflozin 10 mg once daily.

A total of 694 patients were studied; 580 (83.6%) were White, 96 (13.8%) were Black or African American, 5 (0.7%) were of Asian ethnicity, 2 (0.3%) were American Indian or Alaska Native, and 11 (1.6%) were classified otherwise. The mean baseline HbA1c was 9.3%.

The primary endpoint was change in HbA1c from baseline to Week 28.

Efficacy Results:

At Week 28, BYDUREON in combination with dapagliflozin provided statistically significantly greater reductions in HbA1c (-1.77%) compared to BYDUREON alone (-1.42%, p=0.012) and dapagliflozin alone (-1.32%, p=0.001). BYDUREON in combination with dapagliflozin provided statistically significantly greater reductions in FPG (-57.35 mg/dL) compared to BYDUREON alone (-40.53, p <0.001) and dapagliflozin alone (-44.72 mg/dL, p=0.006).

BYDUREON versus Placebo, Both as Add-On to Basal Insulin or Basal Insulin + Metformin Therapy

A 28-week, double-blind, placebo-controlled trial was conducted to compare the safety and efficacy of BYDUREON to placebo when added to basal insulin glargine, with or without metformin, in patients with type 2 diabetes with inadequate glycemic control (Trial 8 - NCT02229383). Patients on sulfonylurea therapy discontinued sulfonylurea. Patients on metformin continued the same dose of metformin. All patients initially entered an 8-week insulin dose-titration phase. Insulin glargine was to be titrated every 3 days with an aim of achieving a target fasting plasma glucose concentration of 72 to 99 mg/dL. Following the titration period, patients with HbA1c ≥7.0% and ≤10.5% were then randomly assigned to receive either BYDUREON 2 mg given subcutaneously once every 7 days (weekly) or placebo once every 7 days (weekly).

A total of 460 patients were studied: 400 (87.0%) were White, 47 (10.2%) were Black or African American, 6 (1.3%) were Asian, 1 (0.2%) was American Indian or Alaska Native, 1 (0.2%) was Pacific Islander, and 5 (1.1%) were classified otherwise.

The primary endpoint was the change in HbA1c from baseline to Week 28.

Efficacy Results:

Compared to placebo, treatment with BYDUREON resulted in a statistically significant reduction in mean HbA1c from baseline to Week 28 (Table 9).

The mean change in fasting plasma glucose from baseline to Week 28 was -12.50 mg/dL for BYDUREON and -2.26 mg/dL for placebo. The mean change from baseline to Week 28 in body weight was -0.92 kg for BYDUREON and +0.38 kg for placebo.

Table 9: Results of 28-Week Trial of BYDUREON versus Placebo, Both as Add-On to Insulin Glargine or Insulin Glargine + Metformin (Trial 8)
 | BYDUREON 2 mg QW | Placebo QW
Intent-to-Treat Population (N) | 231 | 229
Mean HbA1c (%)
Mean Baseline | 8.53 | 8.53
Mean Change at Week 28 [Adjusted LS means and treatment group difference(s) in the change from baseline values at Week 28 using a multiple imputation method that models a “wash-out” for patients having missing data who discontinued treatment. ANCOVA was used with treatment, region, baseline HbA1c stratum (<9.0% or ≥9.0%), and baseline SU-use stratum (yes vs. no) as fixed factors, and baseline value as a covariate.] | -0.88 (0.070) | -0.24 (0.069)
Difference from Placebo [95% CI] | -0.64 [p-value <0.001 (adjusted for multiplicity).]; [-0.83, -0.45]
Percentage Achieving HbA1c <7.0% at Week 28 (%) [Categories are derived from continuous measurements. All patients with missing endpoint data are imputed as non-responders. Treatment comparison is based on Cochran-Mantel-Haenszel (CMH) test stratified by baseline HbA1c (<9.0% or ≥9.0%), and baseline SU use stratum (yes vs. no). P values are from the general association statistics.] | 32.5† | 7.0
N = number of patients in each treatment group, CI = confidence interval, QW = once weekly.
Note: mean change is least squares mean change.

Analyses include measurements post rescue therapy and post premature discontinuation of study medication.

14.5 EXSCEL Cardiovascular Outcomes Trial in Adult Patients with Type 2 Diabetes

EXSCEL was a multinational, placebo-controlled, double-blind, randomized, parallel group pragmatic study that evaluated cardiovascular (CV) outcomes during treatment with BYDUREON (exenatide) for extended-release injectable suspension in adult patients with type 2 diabetes and any level of CV risk when added to the current usual care (NCT01144338).

A total of 14,752 adult patients were randomized 1:1 to either BYDUREON 2 mg given subcutaneously once weekly or placebo and followed as in routine clinical practice for a median of 38.7 months with a median treatment duration of 27.8 months.

Ninety six percent of the patients in both treatment groups completed the study in accordance with the protocol, and the vital status was known at the end of the study for 98.9% and 98.8% of the patients in the BYDUREON and placebo group, respectively. The mean age at study entry was 62 years (21 to 92 years with 8.5% of the patients ≥75 years). Approximately 62.0% of the patients were male, 75.8% were White, 9.8% were Asian, 6.0% were Black or African American, and 20.5% were of Hispanic or Latino ethnicity. The mean BMI was 32.7 kg/m2 and the mean duration of diabetes was 13.1 years. Approximately 49.3% had mild renal impairment (estimated glomerular filtration rate [eGFR] ≥60 to ≤89 mL/min/1.73 m2) and 21.6% had moderate renal impairment (eGFR ≥30 to ≤59 mL/min/1.73 m2).

The mean HbA1c was 8.1%. At baseline, 1.5% of patients were not treated with either oral antidiabetic medications or insulin, 42.3% were treated with one oral antidiabetic medication and 42.4% were treated with two or more oral antidiabetic medications. Usage of oral antidiabetic medications included metformin (76.6%), sulfonylurea (36.6%), dipeptidyl peptidase-4 (DPP-4) inhibitors (14.9%), thiazolidinediones (3.9%), and SGLT2 inhibitors (0.9%). Overall insulin usage was 46.3% (13.8% with insulin alone and 32.6% with insulin and one or more oral antidiabetic medications).

Overall, at baseline, 26.9% of patients did not have established cardiovascular (CV) disease, while 73.1% had established CV disease. The concomitant use of CV medications (e.g., ACE inhibitors, angiotensin receptor blockers, diuretics, beta blockers, calcium channel blockers, antithrombotic and anticoagulants, and lipid-lowering agents) was similar in the BYDUREON and placebo groups. At baseline, the mean systolic blood pressure was 135.5 mmHg, the mean diastolic blood pressure was 78.1 mmHg, the mean LDL was 95.0 mg/dL, and the mean HDL was 44.0 mg/dL.

The primary endpoint in EXSCEL was the time to first confirmed Major Adverse Cardiac Event (MACE) from randomization. MACE was defined as occurrence of either a cardiovascular (CV)-related death, or a nonfatal myocardial infarction (MI) or a nonfatal stroke. All-cause mortality, CV-related death, and fatal or nonfatal MI or stroke, hospitalization for acute coronary syndrome, and hospitalization for heart failure were also assessed as secondary endpoints.

A Cox proportional hazards model was used to test for non-inferiority against the pre-specified risk margin of 1.3 for the hazard ratio of MACE and superiority on MACE if non-inferiority was demonstrated. Type-1 error was controlled across multiple tests using a hierarchical testing strategy.

MACE Results:

BYDUREON did not increase the risk of MACE in adult patients with type 2 diabetes mellitus (HR: 0.91; 95% CI: 0.832, 1.004; P<0.001 for non-inferiority; P=0.06 for superiority). See results in Table 10 and Figure 2. The incidence of MACE in patients with and without established CV disease was 13.4% in the BYDUREON group versus 14.6% in the placebo group and 6.0% (BYDUREON) versus 5.9% (placebo), respectively. Five hundred and seven (507) patients (6.9%) died in the BYDUREON group versus 584 (7.9%) in the placebo group.

Table 10: Analysis of Primary Composite Endpoint MACE and Its Components in Adult Patients with Type 2 Diabetes (EXSCEL)
 | BYDUREON N=7356 | Placebo N=7396 | HR [HR (active/placebo) and CI are based on Cox proportional hazards regression model, stratified by established CV disease, with treatment group only as explanatory variable.] (95% CI)
MACE Composite of CV death, nonfatal MI or nonfatal stroke (time to first confirmed event) | 839 (11.4%) | 905 (12.2%) | 0.91; (0.832, 1.004)
Cardiovascular Death | 340 (4.6%) | 383 (5.2%) | 0.88; (0.76, 1.02)
Nonfatal Myocardial Infarction | 466 (6.3%) | 480 (6.5%) | 0.96; (0.85, 1.09)
Nonfatal Stroke | 169 (2.3%) | 193 (2.6%) | 0.86; (0.70, 1.06)
N=number of patients in each treatment group, HR=hazard ratio, CI=confidence interval, CV=cardiovascular, MI=myocardial infarction.

Figure 2: Time to First Adjudicated MACE in Adult Patients with Type 2 Diabetes (EXSCEL)

HR=hazard ratio, CI=confidence interval.

14.6 Glycemic Control Trial in Pediatric Patients 10 Years of Age and Older with Type 2 Diabetes Mellitus

The efficacy and safety of BYDUREON 2 mg given subcutaneously once weekly or placebo was evaluated in a 24-week randomized, double-blind, placebo-controlled, parallel-group study (Trial 9 - NCT01554618) in 82 patients aged 10 to 17 years with type 2 diabetes treated with diet and exercise alone or in combination with a stable dose of oral antidiabetic agents and/or insulin. This study included a 28-week open-label long-term extension in which patients in both treatment groups received BYDUREON 2 mg given subcutaneously once weekly after the 24-week controlled period.

In this trial, 88% of patients completed the assessment period. The mean age at study entry was 15.1 years (13% were 11 to 12 years old, 59% were 13 to 16 years old and 28% were older than 16 years). Approximately 42% of the patients were male, 43% were White, 4% were Asian, 31% were Black or African American, 6% were American Indian or Alaska Native, and 44% were Hispanic or Latino. The mean body weight was 100.6 kg (67% were in ≥97 weight percentile group, 26% in ≥85 to <97 and 6% in ≥3 to <85), mean BMI was 36.4 kg/m2 and the mean duration of diabetes was 2.3 years.

At baseline, mean HbA1c was 8.17%, 12.2% of patients were not treated with either oral antidiabetic medications or insulin, 40.2% were treated with one oral antidiabetic medication and 1.2% were treated with two oral antidiabetic medications. 79.3% of patients were receiving metformin and 1.2% were receiving sulfonylurea. Overall insulin usage was 46.3% (8.5% with insulin alone and 37.8% with insulin and one other oral antidiabetic medication).

The primary endpoint of the study was the change in HbA1c from baseline to Week 24.

Efficacy Results:

BYDUREON was superior to placebo in reducing HbA1c (Table 11).

The mean changes from baseline to Week 24 for body weight were -0.17 kg with (SE 0.7) and +0.88 kg (SE 1.0) for BYDUREON and placebo, respectively.

Table 11: Results of 24-Week Trial of BYDUREON versus Placebo, Both alone or in Combination with Oral Antidiabetic Agents and/or Insulin in Pediatric Patients 10 Years of Age and Older with Type 2 Diabetes Mellitus (Trial 9)
 | BYDUREON 2 mg QW | Placebo QW
Intent-to-Treat Population (N) | 58 | 24
HbA1c (%)
Mean Baseline | 8.13 | 8.28
Mean Change at Week 24 (SE) [Adjusted LS means and treatment group difference(s) in the change from baseline values at Week 24 using a multiple imputation method that models a “wash-out” for patients having missing data who discontinued treatment. ANCOVA was used with treatment, region as fixed factors, and baseline HbA1c value as a covariate. SE – standard error.] | -0.25 (0.21) | 0.45 (0.29)
Difference from Placebo (95% CI) | -0.71 [p<0.05] (-1.42, 0)
HbA1c<7%
Percentage achieved goal at Week 24 | 31.0 | 8.3
Fasting Plasma Glucose (mg/dL)
Mean Baseline | 165.2 | 170.5
Mean Change at Week 24 (SE) [Adjusted LS means in the change from baseline values at Week 24 using a multiple imputation method that models a “wash-out” for patients having missing data who discontinued treatment. ANCOVA was used with treatment, region, as fixed factors, and baseline FPG value as a covariate.] | -1.3 (8.1) | 16.2 (11.9)

16 HOW SUPPLIED/STORAGE AND HANDLING

How Supplied

- BYDUREON BCISE contains 2 mg of exenatide in 0.85 mL vehicle, in a pre-filled, single-dose autoinjector. Redispersion by mixing provides a white to off-white, opaque, extended-release injectable suspension, available in cartons that contain four single-dose autoinjectors (NDC 0310-6540-04).

Storage and Handling

- BYDUREON BCISE must be stored FLAT.
- Store the autoinjector in the original package. Protect from light. Do not use past the expiration date.
- Store BYDUREON BCISE in the refrigerator at 36°F to 46°F (2°C to 8°C).
- BYDUREON BCISE can be kept at room temperature not to exceed 86°F (30°C) for no more than a total of 4 weeks, if needed.
- Discard BYDUREON BCISE after use in a puncture-resistant container.

17 PATIENT COUNSELING INFORMATION

Advise the patient to read the FDA-approved patient labeling (Medication Guide and Instructions for Use).

Thyroid C-cell Tumors

Inform patients that exenatide extended-release causes benign and malignant thyroid C-cell tumors in rats and that the human relevance of this finding has not been determined. Counsel patients to report symptoms of thyroid tumors (e.g., a lump in the neck, hoarseness, dysphagia, or dyspnea) to their physician [see Boxed Warning and Warnings and Precautions (5.1)].

Acute Pancreatitis

Inform patients of the potential risk for acute pancreatitis and its symptoms: severe abdominal pain that may radiate to the back, and which may or may not be accompanied by vomiting. Instruct patients to discontinue BYDUREON BCISE promptly and contact their physician if pancreatitis is suspected [see Warnings and Precautions (5.2)].

Hypoglycemia with Concomitant Use of Insulin Secretagogues or Insulin

Inform patients that the risk of hypoglycemia is increased when BYDUREON BCISE is used in combination with an agent that induces hypoglycemia, such as a sulfonylurea or insulin. Educate patients on the signs and symptoms of hypoglycemia [see Warnings and Precautions (5.3)].

Acute Kidney Injury Due to Volume Depletion

Inform patients of the potential risk of acute kidney injury due to dehydration associated with gastrointestinal adverse reactions. Advise patients to take precautions to avoid fluid depletion. Inform patients of the signs and symptoms of acute kidney injury and instruct them to promptly report any of these signs or symptoms or persistent (or extended) nausea, vomiting, and diarrhea to their healthcare provider.[see Warnings and Precautions (5.4)].

Severe Gastrointestinal Adverse Reactions

Inform patients of the potential risk of severe gastrointestinal adverse reactions. Instruct patients to contact their healthcare provider if they have severe or persistent gastrointestinal symptoms [see Warnings and Precautions (5.5)].

Hypersensitivity Reactions

Inform patients that serious hypersensitivity reactions have been reported during postmarketing use of exenatide. Inform patients that if symptoms of hypersensitivity reaction occur, stop taking BYDUREON BCISE and seek medical advice promptly [see Warnings and Precautions (5.7)].

Drug-Induced Thrombocytopenia

Inform patients that drug-induced immune-mediated thrombocytopenia has been reported during use of exenatide. Inform patients that if symptoms of thrombocytopenia occur, e.g., bleeding, stop taking BYDUREON BCISE and seek medical advice promptly [see Warnings and Precautions (5.8)].

Serious Injection-Site Reactions

Inform patients that there have been postmarketing reports of serious injection-site reactions with or without subcutaneous nodules, with the use of BYDUREON. Isolated cases of injection-site reactions required surgical intervention. Advise patients to seek medical advice if symptomatic nodules occur, or for any signs or symptoms of abscess, cellulitis, or necrosis [see Warnings and Precautions (5.9)].

Acute Gallbladder Disease

Inform patients of the potential risk for cholelithiasis or cholecystitis. Instruct patients to contact their physician if cholelithiasis or cholecystitis is suspected for appropriate clinical follow-up [see Warnings and Precautions (5.10)].

Pulmonary Aspiration During General Anesthesia or Deep Sedation

Inform patients that BYDUREON BCISE may cause their stomach to empty more slowly which may lead to complications with anesthesia or deep sedation during planned surgeries or procedures. Instruct patients to inform healthcare providers prior to any planned surgeries or procedures if they are taking BYDUREON BCISE [see Warnings and Precautions (5.11)].

Instructions

Train patients on how to use BYDUREON BCISE properly prior to administration. Instruct patients and caregivers on proper mixing and injection technique to ensure the product is adequately mixed and a full dose is delivered. Instruct caregivers to assist pediatric patients with mixing and administration. Refer patients and caregivers to the accompanying Instructions for Use for complete administration instructions with illustrations.

Inform patients formerly on BYETTA who start BYDUREON BCISE that they may experience transient elevations in blood glucose concentrations, which generally improve within the first 4 weeks after initiation of therapy [see Dosage and Administration (2.1)].

Manufactured for:

AstraZeneca Pharmaceuticals LP

Wilmington, DE 19850

By:

Resilience US, Inc.

West Chester, OH 45071

and

Vetter Pharma-Fertigung GmbH & Co. KG

88214 Ravensburg

Germany

BYDUREON, BCISE and BYETTA are trademarks of the AstraZeneca group of companies.

Medication Guide

BYDUREON BCISE® (by-DUR-ee-on B-cise)
(exenatide) extended-release injectable suspension

for subcutaneous use

Read this Medication Guide and the Instructions for Use that comes with BYDUREON BCISE before you start using it and each time you get a refill. There may be new information. This Medication Guide does not take the place of talking with your healthcare provider about your medical condition or your treatment. If you have questions about BYDUREON BCISE after reading this information, ask your healthcare provider or pharmacist.

What is the most important information I should know about BYDUREON BCISE?

BYDUREON BCISE may cause serious side effects, including:

- Possible thyroid tumors, including cancer. Tell your healthcare provider if you get a lump or swelling in your neck, hoarseness, trouble swallowing, or shortness of breath. These may be symptoms of thyroid cancer. In studies with rats, BYDUREON and medicines that work like BYDUREON caused thyroid tumors, including thyroid cancer. It is not known if BYDUREON BCISE will cause thyroid tumors or a type of thyroid cancer called medullary thyroid carcinoma (MTC) in people.
- Do not use BYDUREON BCISE if you or any of your family have ever had a type of thyroid cancer called medullary thyroid carcinoma (MTC), or if you have an endocrine system condition called Multiple Endocrine Neoplasia syndrome type 2 (MEN 2).

What is BYDUREON BCISE?

- BYDUREON BCISE is an injectable prescription medicine that is used along with diet and exercise to improve blood sugar (glucose) in adults and children who are 10 years of age and older with type 2 diabetes mellitus.
- BYDUREON BCISE is not recommended for people who take exenatide or other medicines called glucagon-like peptide 1 (GLP-1) receptor agonist.
- It is not known if BYDUREON BCISE is safe and effective for use in children younger than 10 years of age.

Do not use BYDUREON BCISE if:

- you or any of your family have ever had a type of thyroid cancer called medullary thyroid carcinoma (MTC) or if you have an endocrine system condition called Multiple Endocrine Neoplasia syndrome type 2 (MEN 2).
- you have had a severe allergic reaction to exenatide or any of the ingredients in BYDUREON BCISE. See the end of this Medication Guide for a complete list of ingredients in BYDUREON BCISE. See “What are the possible side effects of BYDUREON BCISE?” for symptoms of a serious allergic reaction. you have a history of low blood platelet count from using exenatide medicines (drug-induced thrombocytopenia).

Before using BYDUREON BCISE, tell your healthcare provider about all of your medical conditions, including if you:

- have or have had problems with your pancreas.
- have severe problems with your stomach, such as slowed emptying of your stomach (gastroparesis) or problems with digesting food.
- are scheduled to have surgery or other procedures that use anesthesia or deep sleepiness (deep sedation).
- are pregnant or plan to become pregnant. It is not known if BYDUREON BCISE will harm your unborn baby. Tell your healthcare provider if you become pregnant while using BYDUREON BCISE. Talk to your healthcare provider about the best way to control your blood sugar if you plan to become pregnant or while you are pregnant.
- are breastfeeding or plan to breastfeed. It is not known if BYDUREON BCISE passes into your breast milk. You should talk with your healthcare provider about the best way to feed your baby while using BYDUREON BCISE.

Tell your healthcare provider about all the medicines you take, including prescription and over-the-counter medicines, vitamins, and herbal supplements. BYDUREON BCISE may affect the way some medicines work and some medicines may affect the way BYDUREON BCISE works.

Before using BYDUREON BCISE, talk to your healthcare provider about low blood sugar and how to manage it. Tell your healthcare provider if you are taking other medicines to treat diabetes, including insulin or sulfonylureas.

Especially tell your healthcare provider if you take warfarin.

Know the medicines you take. Keep a list of them to show your healthcare provider and pharmacist when you get a new medicine.

How should I use BYDUREON BCISE?

- Read the Instructions for Use that comes with BYDUREON BCISE.
- Use BYDUREON BCISE exactly as your healthcare provider tells you to.
- Your healthcare provider should show you how to use BYDUREON BCISE before you use it for the first time.
- Inject BYDUREON BCISE right away after you prepare your dose.
- Caregivers should help children with mixing and injecting BYDUREON BCISE.
- Inject BYDUREON BCISE under the skin (subcutaneously) of your stomach (abdomen), thigh, or upper arm. Do not inject BYDUREON BCISE into a muscle (intramuscularly) or vein (intravenously).
- Use BYDUREON BCISE 1 time each week on the same day each week at any time of the day.
- BYDUREON BCISE may be taken with or without food.
- If you miss a dose of BYDUREON BCISE, take the missed dose as soon as possible if there are at least 3 days (72 hours) until your next scheduled dose. If there are less than 3 days remaining, skip the missed dose and take your next dose on the regularly scheduled day. Do not take 2 doses of BYDUREON BCISE within 3 days of each other.
- You may change the day of the week as long as your last dose was given 3 or more days before.
- If you use a different long acting exenatide medicine and your healthcare provider switches your medicine to BYDUREON BCISE, you should start using BYDUREON BCISE at your next scheduled dose.
- Do not mix insulin and BYDUREON BCISE together in the same injection.
- You may give an injection of BYDUREON BCISE and insulin in the same body area (such as, your stomach area), but not right next to each other.
- Change (rotate) your injection site with each weekly injection. Do not use the same site for each injection.
- Do not share your BYDUREON BCISE pen with other people, even if the needle has been changed. You may give other people a serious infection or get a serious infection from them.
- If you take too much BYDUREON BCISE, call your healthcare provider or Poison Help line at 1-800-222-1222 or go to the nearest hospital emergency room right away.

What are the possible side effects of BYDUREON BCISE?

BYDUREON BCISE may cause serious side effects, including:

- See "What is the most important information I should know about BYDUREON BCISE?"
- inflammation of your pancreas (pancreatitis). Stop using BYDUREON BCISE and call your healthcare provider right away if you have severe pain in your stomach area (abdomen) that will not go away, with or without vomiting. You may feel the pain from your abdomen to your back.
- low blood sugar (hypoglycemia). Your risk for getting low blood sugar may be higher if you use BYDUREON BCISE with another medicine that can cause low blood sugar, such as a sulfonylurea or insulin. Signs and symptoms of low blood sugar may include:

∘ dizziness or light-headedness
∘ sweating
∘ confusion or drowsiness
∘ headache

∘ blurred vision
∘ slurred speech
∘ shakiness
∘ fast heartbeat

∘ anxiety, irritability, or mood changes
∘ hunger
∘ weakness
∘ feeling jittery

- dehydration leading to kidney problems. Diarrhea, nausea, and vomiting may cause a loss of fluids (dehydration) which may cause kidney problems. It is important for you to drink fluids to help reduce your chance of dehydration. Tell your healthcare provider right away if you have nausea, vomiting, or diarrhea that does not go away.
- severe stomach problems. Stomach problems, sometimes severe, have been reported in people who use BYDUREON BCISE. Tell your healthcare provider if you have stomach problems that are severe or will not go away.
- serious allergic reactions. Stop using BYDUREON BCISE and get medical help right away if you have any symptoms of a serious allergic reaction, including
  ∘ swelling of your face, lips, tongue or throat
  ∘ fainting or feeling dizzy
  ∘ problems breathing or swallowing
  ∘ severe rash or itching
  ∘ very rapid heartbeat
- low blood platelet count (drug-induced thrombocytopenia). BYDUREON BCISE may cause the number of platelets in your blood to be reduced. When your platelet count is too low, your body cannot form blood clots. You could have serious bleeding that could lead to death. Stop using BYDUREON BCISE and call your healthcare provider right away if you have unusual bleeding or bruising. Your blood platelet count may continue to be low for about 10 weeks after stopping BYDUREON BCISE.
- serious injection-site reactions. Serious injection-site reactions, with or without bumps (nodules), have happened in some people who use BYDUREON BCISE. Some of these injection-site reactions have required surgery. Call your healthcare provider if you have any symptoms of an injection-site reaction, including severe pain, swelling, blisters, an open wound, a dark scab.
- gallbladder problems. Gallbladder problems have happened in some people who take BYDUREON BCISE. Tell your healthcare provider right away if you get symptoms of gallbladder problems which may include:
  ∘ pain in your upper stomach (abdomen)
  ∘ fever
  ∘ yellowing of skin or eyes (jaundice)
  ∘ clay colored stools
- food or liquid getting into the lungs during surgery or other procedures that use anesthesia or deep sleepiness (deep sedation). BYDUREON BCISE may increase the chance of food getting into your lungs during surgery or other procedures. Tell all your healthcare providers that you are taking BYDUREON BCISE before you are scheduled to have surgery or other procedures.

The most common side effects of BYDUREON BCISE may include a bump (nodule) at the injection site and nausea.

Talk to your healthcare provider about any side effect that bothers you or does not go away.

These are not all the possible side effects of BYDUREON BCISE.

Call your doctor for medical advice about side effects. You may report side effects to FDA at 1‑800-FDA-1088.

Keep BYDUREON BCISE and all medicines out of the reach of children.

General information about the safe and effective use of BYDUREON BCISE.

Medicines are sometimes prescribed for purposes other than those listed in a Medication Guide. Do not use BYDUREON BCISE for a condition for which it was not prescribed. Do not give your BYDUREON BCISE to other people, even if they have the same symptoms you have. It may harm them.

You can ask your pharmacist or healthcare provider for information about BYDUREON BCISE that is written for health professionals.

What are the ingredients in BYDUREON BCISE?

Contents of the powder:

Active ingredient: exenatide.

Inactive ingredients: polylactide-co-glycolide and sucrose.

Contents of liquid (diluent):

Inactive ingredients: medium chain triglycerides.

BYDUREON, BCISE and BYETTA are trademarks of the AstraZeneca group of companies. All other marks are the marks of their respective owners.

Manufactured for:
AstraZeneca Pharmaceuticals LP
Wilmington, DE 19850

By:
Resilience US, Inc.
West Chester, OH 45071 and

Vetter Pharma-Fertigung GmbH & Co. KG

88214 Ravensburg

Germany

For more information about BYDUREON BCISE, go to www.BYDUREONBCISE.com or call 1‑800‑236‑9933.

This Medication Guide has been approved by the U.S. Food and Drug Administration. Revised: 05/2025

INSTRUCTIONS FOR USE

BYDUREON BCISE® (by-DUR-ee-on B-cise)

(exenatide) extended-release injectable suspension

for subcutaneous use

once-weekly

Read the Instructions for Use before you start using BYDUREON BCISE.
Before using BYDUREON BCISE, talk to your healthcare provider about how to use it the right way.

Caregivers should help children with mixing and injecting BYDUREON BCISE.

Before You Begin

The autoinjector:

- Is a single use, fixed dose autoinjector that automatically injects your medicine.
- Is injected 1 time per week under the skin.
- Comes in the locked position before you use it. Do not unlock the autoinjector until you are ready to inject it.
- Needle is hidden. You do not see it before, during, or after using the autoinjector.
- Do not use the autoinjector if any parts look to be broken or damaged.
- Store flat in the refrigerator between 36°F to 46°F (2°C to 8°C).
- BYDUREON BCISE should not be used by people who are blind or cannot see well, unless another person who is trained to use this device can help.
- Keep the autoinjector, and all medicines, out of the reach of children.

Before Use

Supplies needed to give your injection:

● BYDUREON BCISE autoinjector ● Alcohol swab ● A clean, flat surface ● Sharps container (see “disposal” instructions at the end of these instructions)

Step 1: Prepare for Injection

A. Let your autoinjector come to room temperature.
Remove 1 autoinjector from the refrigerator and rest it flat for 15 minutes.
Autoinjector can be kept at room temperature for up to 4 weeks.

B. Check the expiration date (labeled EXP) printed on the autoinjector label.
Do not use the autoinjector past the expiration date. If the expiration date has passed, throw it away and get a new autoinjector.

C. Wash your hands.

D. Choose your injection site.
You can inject into your stomach, thigh, or back of the upper arm, see Figure D.

Each week you can use the same area of your body, but choose a different injection site in that area of your body.
Clean the area with an alcohol swab.

Figure D

Step 2: Mix the medicine

A. Look in the window.
You may see white medicine along the sides, bottom or top. This means the medicine is not mixed evenly.

B. Shake the autoinjector hard,
in an up-and-down motion, until the medicine is mixed evenly and you do not see any white medicine along the sides, bottom or top.

•Shake for at least 15 seconds.

• The autoinjector may need to be shaken longer than 15 seconds if the autoinjector has not been correctly stored flat.

C. Check the mix.
Hold the autoinjector up to the light and look through both sides and the bottom of the window. If not mixed well, repeat Step 2 and check again.

Do not go to the next step unless your medicine is mixed well. To get a full dose, the medicine must be mixed well and look cloudy.
If not mixed well, continue to shake hard.

Step 3: Prepare the Autoinjector

Important: After the medicine is fully mixed, you must complete the preparation steps right away, and inject to get the full dose. Do not save it to use later.

Only unlock the autoinjector when you are ready to inject

A. Unlock the autoinjector.
Hold the autoinjector up straight with the orange cap toward the ceiling. Turn the knob from the Lock to the Unlock position until you hear a click.

B. While still holding the autoinjector straight up, firmly unscrew the orange cap.

- You may need to turn the cap a few times before it loosens (if you hear clicking you are turning in the wrong direction).
- Continue holding the autoinjector upright to prevent the medicine from accidently leaking.
- A green shield will pop up after the cap is removed. The green shield hides the needle.

It is normal to see a few drops of liquid inside the cap. Do not recap the autoinjector.
Throw away the cap.

Step 4: Inject the Dose

A. Inject and hold:

- Push the autoinjector against your skin. You will hear a “click” when the injection begins.
- Keep holding the autoinjector against the skin for 15 seconds. This is to make sure you get the full dose.

B. Make sure you received your full dose.
After you receive your injection, you will see an orange rod in the window. After you lift the autoinjector from your skin, the green shield will move back up to lock over the needle. See the Common Questions and Answers for what to do if you do not see the orange rod in the window after injection.

Step 4: Inject the Dose (continued)

C. Disposal.
Put your used autoinjector in a FDA-cleared sharps disposal container right away after use.
Do not throw away (dispose of) loose needles and syringes into your household trash. If you do not have an FDA-cleared sharps disposal container, you may use a household container that is:

- Made of heavy-duty plastic
- Can be closed with a tight-fitting, puncture-resistant lid that will not let sharps come out
- Upright and stable during use
- Leak-resistant, and
- Properly labeled to warn of hazardous waste inside the container

When your sharps disposal container is almost full, you will need to follow your community guidelines for the right way to dispose of your sharps disposal container. There may be state or local laws about how you should throw away used needles and syringes. For more information about safe sharps disposal, and for specific information about sharps disposal in the state that you live in, go to FDA’s website at: http://www.fda.gov/safesharpsdisposal.

Do not dispose of your used sharps disposal container in your household trash unless your community guidelines permit this. Do not recycle your used sharps disposal container. See “Common Questions and Answers” for additional disposal information.

Please keep these instructions to use for your next dose.

Common Questions and Answers

1. Where is the needle?
The needle is attached to the autoinjector and covered by the orange cap.
When you unscrew the orange cap, the green shield keeps the needle covered until you inject.
For more information, please see Figure N in Step 3B in the Instructions for Use.

2. How do I know if the medicine is fully mixed?
After shaking the autoinjector, look through both sides of the window. You should not see any white medicine along the bottom, top, or sides. If you see white medicine, it is unmixed. To mix, shake the autoinjector hard until the white medicine is no longer on the bottom, top, or sides. The medicine should look even throughout.

3. Why do I need to hold the autoinjector upright while removing the orange cap?
Holding the autoinjector with the orange cap straight up helps prevent the medicine from leaking. It is normal to see a few drops of medicine inside the orange cap after you unscrew it.

4. Why should I inject my medicine right away after mixing it?
If you do not inject your medicine right away after mixing, the medicine may separate, and you will not get your full dose. You can re-mix your medicine if your autoinjector is in the locked position. However, after you unlock it, you must complete the preparation steps right away and inject to get the full dose. You cannot save it for later use.

5. How do I know I gave myself the full dose of medicine?
To be sure you get your full dose, press and hold the autoinjector against your skin.
You will feel the needle go into your skin. Hold the needle against your skin for 15 seconds. This will allow enough time for all the medicine to go from the autoinjector to under your skin. After removing the needle, look for the orange rod in the window as a way to tell that the dose has been given. If the orange rod does not appear contact Customer Service at 1-800-236-9933.

6. Why should I store my autoinjectors flat in the refrigerator?
Autoinjectors stored vertically (with the needle up or down) are more difficult to mix. The medicine can still be fully mixed, but it will take more shaking and more time.

7. What if I do not have an FDA-cleared sharps disposal container?
Do not throw away (dispose of) the autoinjector in your household trash. If you do not have an FDA-cleared sharps disposal container, you may use a household container that is:

- Made of heavy-duty plastic
- Can be closed with a tight-fitting, puncture-resistant lid, that will not let sharps come out
- Upright and stable during use
- Leak-resistant, and
- Properly labeled to warn of hazardous waste inside the container

When your sharps disposal container is almost full, you will need to follow your community guidelines for the right way to dispose of your sharps disposal container. There may be state or local laws about how you should throw away used needles and autoinjectors.

For more information about safe sharps disposal, and for specific information about sharps disposal in the state you live in, go to the FDA’s website at: http://www.fda.gov/safesharpsdisposal.

8. What if I cannot unlock the autoinjector?
Review the Instructions for Use Step 3 to make sure you are following the right instructions, then contact Customer Service, 1-800-236-9933 for help as needed. Do not try to unlock with excessive force or tools.

9. What if I cannot remove the orange cap from the autoinjector?
Review the Instructions for Use Step 3 to make sure you are following the right instructions. You should also check that the knob is fully in the unlocked position, then contact Customer Service, 1-800-236-9933 for help as needed. Do not use tools or try to force the cap off.

10. For other questions about BYDUREON BCISE:
Visit www.BydureonBCise.com.
Call Customer Service at 1-800-236-9933.

How to Store BYDUREON BCISE Autoinjector

- Store the autoinjector flat in the refrigerator between 36°F to 46°F (2°C to 8°C).
- Each autoinjector can be kept at room temperature not to exceed 86°F (30°C) for no more than a total of 4 weeks, if needed.
- Store in the packaging provided to protect from light until you are ready to prepare and use your dose.
- Do not use the autoinjector past the expiration date. The expiration date is labeled EXP.
- Keep the autoinjector clean and away from spills.
This Instructions for Use has been approved by the U.S. Food and Drug Administration. Revised: 03/2024

Package/Label Display Panel – 2mg Pen Label

NDC 0310-6540-01
2 mg single-dose autoinjector

Medication requires mixing before use

Store FLAT in a refrigerator 36-46°F

(2-8°C)

Once-weekly

BYDUREON BCise®
(exenatide) extended-release

injectable suspension

For subcutaneous use only

Rx only AstraZeneca

Package/Label Display Panel -2mg pen carton

NDC 0310-6540-04
Once-Weekly

BYDUREON BCise® 2 mg single-dose autoinjector
(exenatide) extended-release

injectable suspension

For subcutaneous use only

Dispense with enclosed Medication Guide

to each patient.

Store FLAT in refrigerator 36-46°F (2-8°C).

Total Quantity: 4 x Single-Dose Autoinjectors
Use one autoinjector every week

Each autoinjector delivers a 2 mg dose

Rx only AstraZeneca